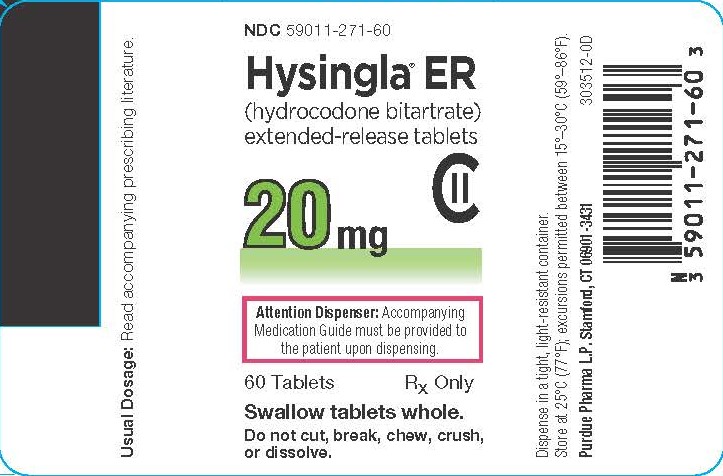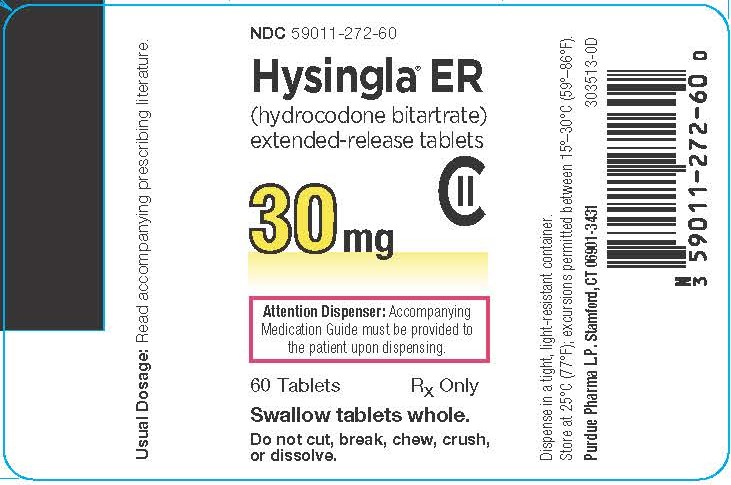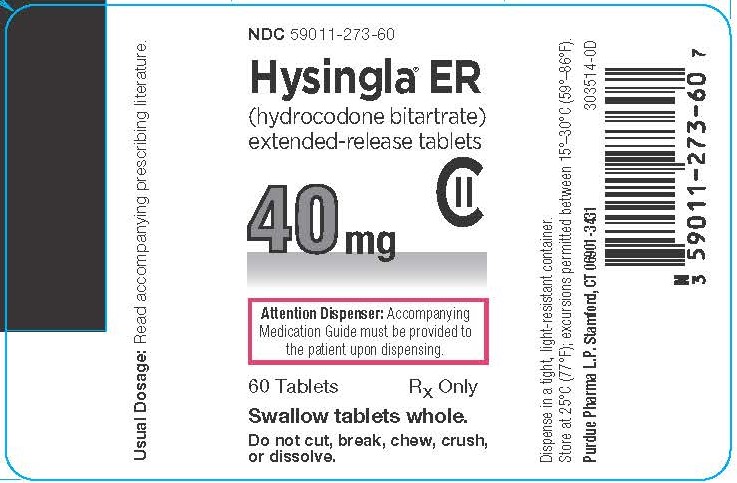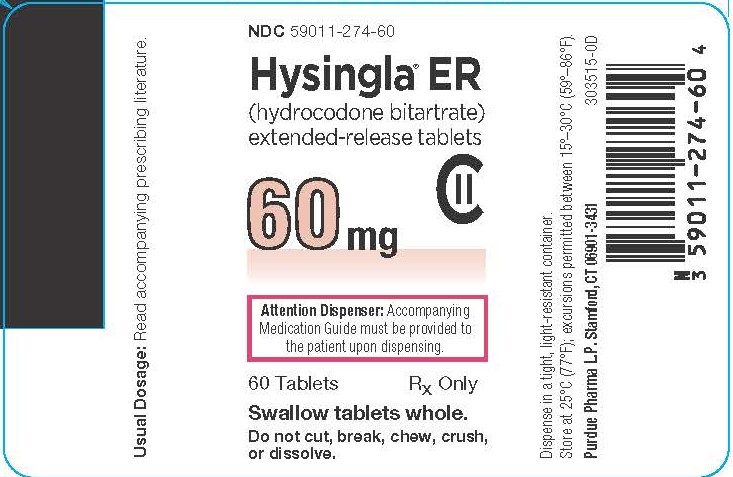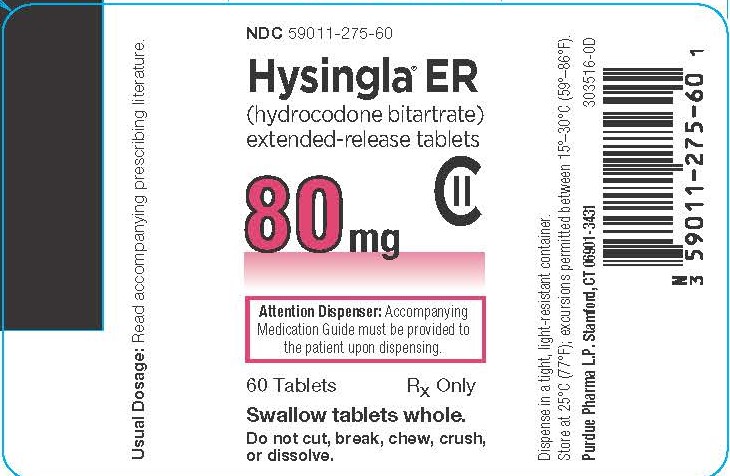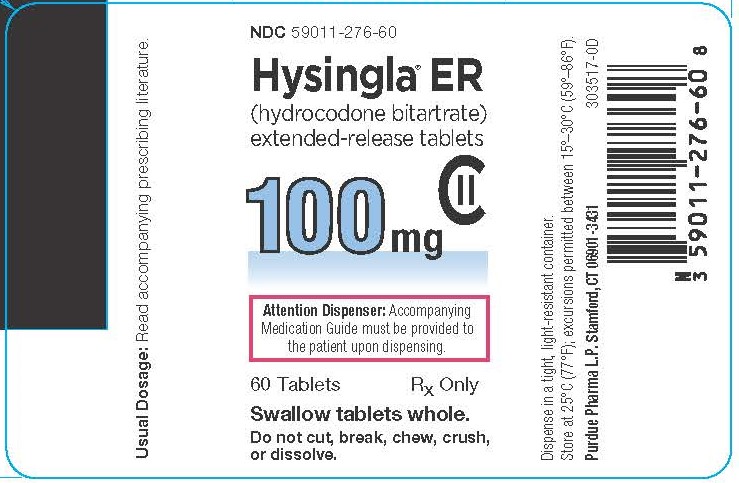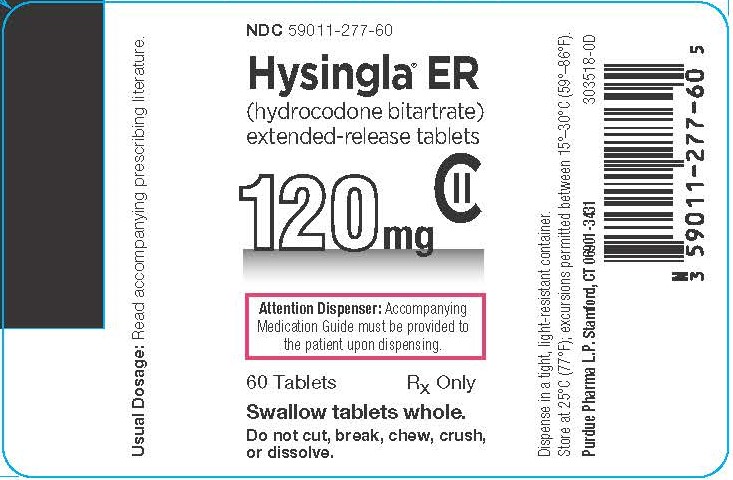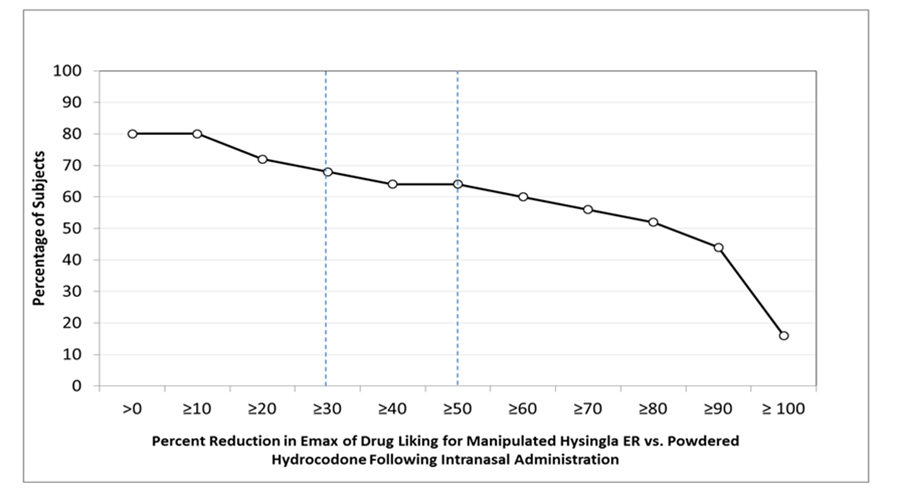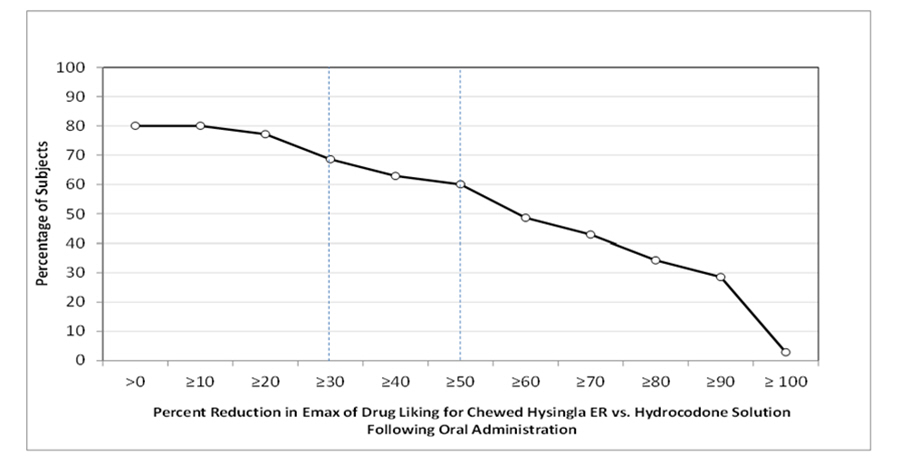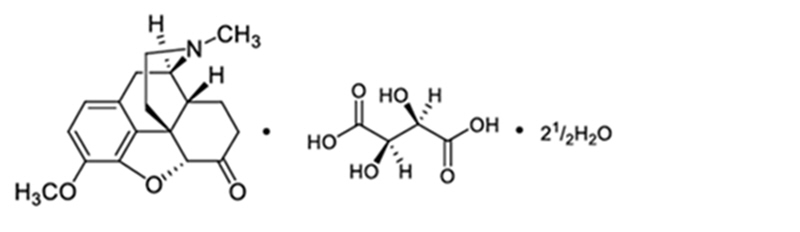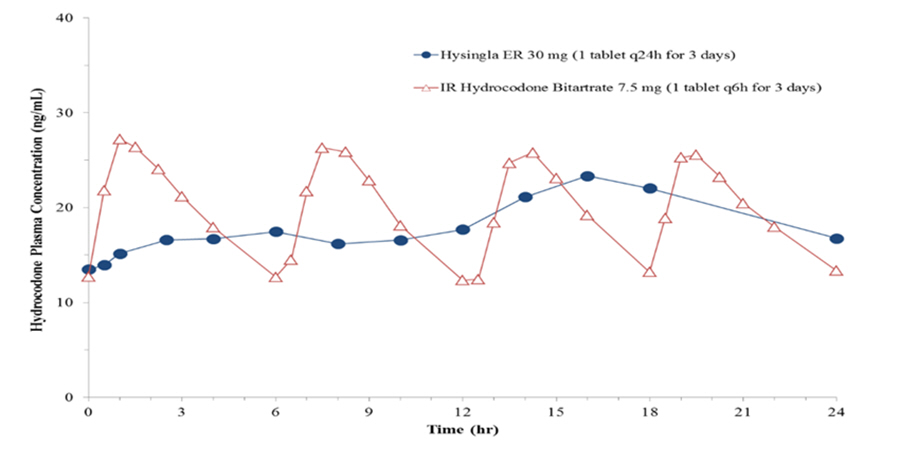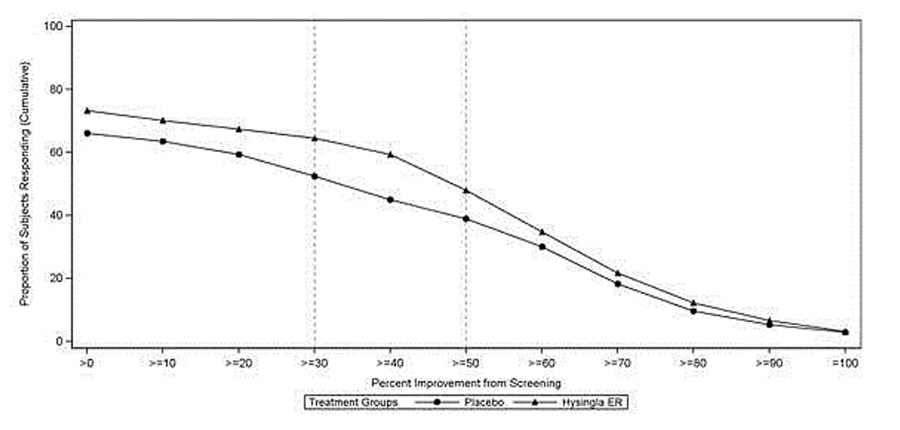 DRUG LABEL: Hysingla ER
NDC: 59011-272 | Form: TABLET, EXTENDED RELEASE
Manufacturer: Purdue Pharma LP
Category: prescription | Type: HUMAN PRESCRIPTION DRUG LABEL
Date: 20260113
DEA Schedule: CII

ACTIVE INGREDIENTS: HYDROCODONE BITARTRATE 30 mg/1 1
INACTIVE INGREDIENTS: POLYETHYLENE GLYCOL 3350; MICROCRYSTALLINE CELLULOSE; POLYSORBATE 80; POLYVINYL ALCOHOL, UNSPECIFIED; TALC; TITANIUM DIOXIDE; FERRIC OXIDE YELLOW; MAGNESIUM STEARATE; BUTYLATED HYDROXYTOLUENE; HYDROXYPROPYL CELLULOSE (1600000 WAMW); POLYETHYLENE GLYCOL, UNSPECIFIED

HIGHLIGHTS OF PRESCRIBING INFORMATION

These highlights do not include all the information needed to use HYSINGLA® ER safely and effectively. See full prescribing information for HYSINGLA ER.
HYSINGLA® ER (hydrocodone bitartrate) extended-release tablets, for oral use, CII
Initial U.S. Approval: 1943

WARNING: SERIOUS AND LIFE-THREATENING RISKS FROM USE OF HYSINGLA ER

See full prescribing information for complete boxed warning.

- HYSINGLA ER exposes users to risks of addiction, abuse, and misuse, which can lead to overdose and death. Assess patient's risk before prescribing, and reassess regularly for these behaviors and conditions. (5.1)
- Serious, life-threatening, or fatal respiratory depression may occur, especially upon initiation or following a dosage increase. To reduce the risk of respiratory depression, proper dosing and titration of HYSINGLA ER are essential. Instruct patients to swallow HYSINGLA ER whole to avoid exposure to a potentially fatal dose of hydrocodone. (5.2)
- Accidental ingestion of HYSINGLA ER, especially by children, can result in fatal overdose of hydrocodone. (5.2)
- Concomitant use of opioids with benzodiazepines or other central nervous system (CNS) depressants, including alcohol, may result in profound sedation, respiratory depression, coma, and death. Reserve concomitant prescribing for use in patients for whom alternative treatment options are inadequate. (5.3, 7)
- Advise pregnant women using opioids for an extended period of time of the risk of Neonatal Opioid Withdrawal Syndrome, which may be life-threatening if not recognized and treated. Ensure that management by neonatology experts will be available at delivery (5.4)
- Healthcare providers are strongly encouraged to complete a REMS-compliant education program and to counsel patients and caregivers on serious risks, safe use, and the importance of reading the Medication Guide with each prescription. (5.5)
- Concomitant use with CYP3A4 inhibitors (or discontinuation of CYP3A4 inducers) can result in a fatal overdose of hydrocodone. (5.6, 7, 12.3)

RECENT MAJOR CHANGES

Boxed Warning | 12/2025
Indications and Usage (1) | 12/2025
Dosage and Administration (2.2, 2.3, 2.7) | 12/2025
Warnings and Precautions (5.1, 5.2, 5.3, 5.14, 5.16) | 12/2025

1 INDICATIONS AND USAGE

HYSINGLA ER is an opioid agonist indicated for the management of severe and persistent pain that requires an opioid analgesic and that cannot be adequately treated with alternative options, including immediate-release opioids. (1)

Limitations of Use

- Because of the risks of addiction, abuse, misuse, overdose, and death, which can occur at any dosage or duration and persist over the course of therapy, reserve opioid analgesics, including HYSINGLA ER, for use in patients for whom alternative treatment options are ineffective, not tolerated, or would be otherwise inadequate to provide sufficient management of pain. (1, 5.1)
- HYSINGLA ER is not indicated as an as-needed (prn) analgesic. (1)

2 DOSAGE AND ADMINISTRATION

- HYSINGLA ER should be prescribed only by healthcare professionals who are knowledgeable about the use of extended-release/long-acting opioids and how to mitigate the associated risks. (2.1)
- Daily doses of HYSINGLA ER greater than or equal to 80 mg are only for use in patients in whom tolerance to an opioid of comparable potency has been established. (2.1)
- Patients considered opioid-tolerant are those taking, for one week or longer, at least 60 mg oral morphine per day, 25 mcg transdermal fentanyl per hour, 30 mg oral oxycodone per day, 8 mg oral hydromorphone per day, 25 mg oral oxymorphone per day, 60 mg oral hydrocodone per day, or an equianalgesic dose of another opioid. (2.1)
- Use the lowest effective dosage for the shortest duration consistent with individual patient treatment goals (2.1).
- Reserve titration to higher doses of HYSINGLA ER for patients in whom lower doses are insufficiently effective and in whom the expected benefits of using higher dose opioid clearly outweigh the substantial risks. (2.1, 5.1)
- Initiate the dosing regimen for each patient individually, taking into account the patient's underlying cause and severity of pain, prior analgesic treatment and response, and risk factors for addiction, abuse, and misuse. (2.1, 5.1)
- Respiratory depression can occur at any time during opioid therapy, especially when initiating and following dosage increases with HYSINGLA ER. Consider this risk when selecting an initial dose and when making dose adjustments. (2.1, 5.2)
- HYSINGLA ER is administered orally once daily (every 24 hours). (2.1)
- Instruct patients to swallow HYSINGLA ER intact, and not to crush, chew, or dissolve the tablets (risk of potentially fatal overdose). (2.1, 5.1)
- Instruct patients to take tablets one at a time, with enough water to ensure complete swallowing immediately after placing in the mouth (2.1, 5.13)
- For patients who are not opioid tolerant, initiate with 20 mg tablets orally every 24 hours. (2.3)
- Discuss opioid overdose reversal agents and options for acquiring them with the patient and/or caregiver, both when initiating and renewing treatment with HYSINGLA ER, especially if the patient has additional risk factors for overdose, or close contacts at risk for exposure and overdose. (2.2, 5.1, 5.2, 5.3)
- To convert to HYSINGLA ER from another opioid, follow the conversion instructions to obtain an estimated dose. (2.3)
- Dose titration of HYSINGLA ER may occur every 3 to 5 days (2.4)
- Periodically reassess patients receiving HYSINGLA ER to evaluate the continued need for opioid analgesics to maintain pain control, for the signs or symptoms of adverse reactions, and for the development of addiction, abuse, or misuse. (2.4)
- Patients with Severe Hepatic Impairment: Initiate dosing with one half of the recommended starting dosage and titrate carefully. Regularly evaluate for respiratory depression, sedation, and hypotension. (2.5)
- Patients with Moderate to Severe Renal Impairment and End-Stage Renal Disease: Initiate dosing at one half the recommended starting dosage and titrate carefully. Regularly evaluate for signs of respiratory depression, sedation, and hypotension. (2.6)
- Do not rapidly reduce or abruptly discontinue HYSINGLA ER in a physically-dependent patient because rapid reduction or abrupt discontinuation of opioid analgesics has resulted in serious withdrawal symptoms, uncontrolled pain, and suicide. (2.7, 5.16)

3 DOSAGE FORMS AND STRENGTHS

Extended-release tablets: 20, 30, 40, 60, 80, 100, and 120 mg (3)

4 CONTRAINDICATIONS

- Significant respiratory depression (4)
- Acute or severe bronchial asthma in an unmonitored setting or in the absence of resuscitative equipment (4)
- Known or suspected gastrointestinal obstruction, including paralytic ileus (4)
- Hypersensitivity to hydrocodone or to any other components of HYSINGLA ER (4)

5 WARNINGS AND PRECAUTIONS

- Opioid-Induced Hyperalgesia and Allodynia: Opioid-Induced Hyperalgesia (OIH) occurs when an opioid analgesic paradoxically causes an increase in pain, or an increase in sensitivity to pain. If OIH is suspected, carefully consider appropriately decreasing the dose of the current opioid analgesic, or opioid rotation. (5.7)
- Life-Threatening Respiratory Depression in Patients with Chronic Pulmonary Disease or in Elderly, Cachectic, or Debilitated Patients: Regularly evaluate, particularly during initiation and titration. (5.8)
- Adrenal Insufficiency: If diagnosed, treat with physiologic replacement of corticosteroids, and wean patient off of the opioid. (5.9)
- Severe Hypotension: Regularly evaluate during dosage initiation and titration. Avoid use of HYSINGLA ER in patients with circulatory shock. (5.10)
- QTc Prolongation: Avoid use in patients with congenital long QTc syndrome. In patients who develop QTc prolongation, consider reducing the dose. (5.11, 12.2)
- Risks of Use in Patients with Increased Intracranial Pressure, Brain Tumors, Head Injury, or Impaired Consciousness: Monitor for sedation and respiratory depression. Avoid use of HYSINGLA ER in patients with circulatory shock. (5.12)
- Risk of Obstruction in Patients who have Difficulty Swallowing or have Underlying GI Disorders that may Predispose them to Obstruction: Consider use of an alternative analgesic. (5.14)

6 ADVERSE REACTIONS

Most common treatment-emergent adverse events (incidence ≥ 5%) are constipation, nausea, vomiting, fatigue, upper respiratory tract infection, dizziness, headache, and somnolence. (6.1)

To report SUSPECTED ADVERSE REACTIONS, contact Purdue Pharma L.P. at 1-888-726-7535 or FDA at 1-800-FDA-1088 or www.fda.gov/medwatch.

7 DRUG INTERACTIONS

- Serotonergic Drugs: Concomitant use may result in serotonin syndrome. Discontinue HYSINGLA ER if serotonin syndrome is suspected. (7)
- Mixed Agonists/Antagonists and Partial Agonist Opioid Analgesics: Avoid use with HYSINGLA ER because they may reduce analgesic effect of HYSINGLA ER or precipitate withdrawal symptoms. (7)
- Monoamine Oxidase Inhibitors (MAOIs): Can potentiate the effects of hydrocodone. Avoid concomitant use in patients receiving MAOIs or within 14 days of stopping an MAOI. (7)

8 USE IN SPECIFIC POPULATIONS

- Pregnancy: May cause fetal harm. (8.1)
- Lactation: Not recommended. (8.2)

FULL PRESCRIBING INFORMATION

WARNING: SERIOUS AND LIFE-THREATENING RISKS FROM USE OF HYSINGLA ER

Addiction, Abuse, and Misuse

Because the use of HYSINGLA ER exposes patients and other users to the risks of opioid addiction, abuse, and misuse, which can lead to overdose and death, assess each patient's risk prior to prescribing and reassess all patients regularly for the development of these behaviors and conditions [see Warnings and Precautions (5.1)].

Life-Threatening Respiratory Depression

Serious, life-threatening, or fatal respiratory depression may occur with use of HYSINGLA ER, especially during initiation or following a dosage increase. To reduce the risk of respiratory depression, proper dosing and titration of HYSINGLA ER are essential. Instruct patients to swallow HYSINGLA ER tablets whole; crushing, chewing, or dissolving HYSINGLA ER tablets can cause rapid release and absorption of a potentially fatal dose of hydrocodone [see Warnings and Precautions (5.2)].

Accidental Ingestion

Accidental ingestion of even one dose of HYSINGLA ER, especially by children, can result in a fatal overdose of hydrocodone [see Warnings and Precautions (5.2)].

Risks From Concomitant Use With Benzodiazepines Or Other CNS Depressants

Concomitant use of opioids with benzodiazepines or other central nervous system (CNS) depressants, including alcohol, may result in profound sedation, respiratory depression, coma, and death. Reserve concomitant prescribing of HYSINGLA ER and benzodiazepines or other CNS depressants for use in patients for whom alternative treatment options are inadequate [see Warnings and Precautions (5.3), Drug Interactions (7)].

Neonatal Opioid Withdrawal Syndrome (NOWS)

Advise pregnant women using opioids for an extended period of time of the risk of Neonatal Opioid Withdrawal Syndrome, which may be life-threatening if not recognized and treated. Ensure that management by neonatology experts will be available at delivery [see Warnings and Precautions (5.4)].

Opioid Analgesic Risk Evaluation and Mitigation Strategy (REMS)

Healthcare providers are strongly encouraged to complete a REMS-compliant education program and to counsel patients and caregivers on serious risks, safe use, and the importance of reading the Medication Guide with each prescription [see Warnings and Precautions (5.5)].

Cytochrome P450 3A4 Interaction

The concomitant use of HYSINGLA ER with all cytochrome P450 3A4 inhibitors may result in an increase in hydrocodone plasma concentrations, which could increase or prolong adverse reactions and may cause potentially fatal respiratory depression. In addition, discontinuation of a concomitantly used cytochrome P450 3A4 inducer may result in an increase in hydrocodone plasma concentration. Regularly evaluate patients receiving HYSINGLA ER and any CYP3A4 inhibitor or inducer [see Warnings and Precautions (5.6), Drug Interactions (7), and Clinical Pharmacology (12.3)].

1 INDICATIONS AND USAGE

HYSINGLA ER is indicated for the management of severe and persistent pain that requires an opioid analgesic and that cannot be adequately treated with alternative options, including immediate-release opioids.

Limitations of Use

- Because of the risks of addiction, abuse, misuse, overdose and death, which can occur at any dosage or duration and persist over the course of therapy [see Warnings and Precautions (5.1)], reserve opioid analgesics, including HYSINGLA ER, for use in patients for whom alternative treatment options are ineffective, not tolerated, or would be otherwise inadequate to provide sufficient management of pain.
- HYSINGLA ER is not indicated as an as-needed (prn) analgesic.

2 DOSAGE AND ADMINISTRATION

2.1 Important Dosage and Administration Instructions

- HYSINGLA ER should be prescribed only by healthcare professionals who are knowledgeable about the use of extended-release/long-acting opioids and how to mitigate the associated risks.
- Daily doses of HYSINGLA ER greater than or equal to 80 mg are only for use in patients in whom tolerance to an opioid of comparable potency has been established. Patients who are opioid tolerant are those receiving, for one week or longer, at least 60 mg oral morphine per day, 25 mcg transdermal fentanyl per hour, 30 mg oral oxycodone per day, 8 mg oral hydromorphone per day, 25 mg oral oxymorphone per day, 60 mg oral hydrocodone per day, or an equianalgesic dose of another opioid.
- Use the lowest effective dosage for the shortest duration of time consistent with individual patient treatment goals [see Warnings and Precautions (5)]. Because the risk of overdose increases as opioid doses increase, reserve titration to higher doses of HYSINGLA ER for patients in whom lower doses are insufficiently effective and in whom the expected benefits of using a higher dose opioid clearly outweigh the substantial risks.
- Initiate the dosing regimen for each patient individually, taking into account the patient's underlying cause and severity of pain, prior analgesic treatment and response, and risk factors for addiction, abuse, and misuse [see Warnings and Precautions (5.1)].
- Respiratory depression can occur at any time during opioid therapy, especially when initiating and following dosage increases with HYSINGLA ER. Consider this risk when selecting an initial dose and when making dose adjustments [see Warnings and Precautions (5.2)].
- HYSINGLA ER is administered orally once daily (every 24 hours). Multiple tablets of lower dose strengths that provide the desired total daily dose can be taken as a once daily dose.
- Instruct patients to swallow HYSINGLA ER tablets whole, one tablet at a time, with enough water to ensure complete swallowing immediately after placing in the mouth. Instruct patients not to pre-soak, lick, or otherwise wet the tablet prior to placing in the mouth [see Warnings and Precautions (5.13)]. Crushing, chewing, or dissolving HYSINGLA ER tablets will result in uncontrolled delivery of hydrocodone and can lead to overdose or death [see Warnings and Precautions (5.1)].

2.2 Patient Access to an Opioid Overdose Reversal Agent for the Emergency Treatment of Opioid Overdose

Inform patients and caregivers about opioid overdose reversal agents (e.g., naloxone, nalmefene). Discuss the importance of having access to an opioid overdose reversal agent, especially if the patient has risk factors for overdose (e.g., concomitant use of CNS depressants, a history of opioid use disorder, or prior opioid overdose) or if there are household members (including children) or other close contacts at risk for accidental ingestion or opioid overdose. The presence of risk factors for overdose should not prevent the management of pain in any patient [see Warnings and Precautions (5.1, 5.2, 5.3)].

Discuss the options for obtaining an opioid overdose reversal agent (e.g., prescription, over-the-counter, or as part of a community-based program) [see Warnings and Precautions (5.2)].

There are important differences among the opioid overdose reversal agents, such as route of administration, product strength, approved patient age range, and pharmacokinetics. Be familiar with these differences, as outlined in the approved labeling for those products, prior to recommending or prescribing such an agent.

2.3 Initial Dosage

It is safer to underestimate a patient's 24-hour oral hydrocodone dosage and provide rescue medication (e.g., immediate-release opioid) than to overestimate the 24-hour oral hydrocodone dosage and manage an adverse reaction due to an overdose. While useful tables of opioid equivalents are readily available, there is inter-patient variability in the potency of opioid drugs and opioid formulations. Frequently reevaluate patients for signs and symptoms of opioid withdrawal and for signs of oversedation/toxicity after converting patients to HYSINGLA ER.

Use of HYSINGLA ER in Patients who are not Opioid Tolerant

The starting dose for patients who are not opioid tolerant is HYSINGLA ER 20 mg orally every 24 hours. Use of higher starting doses in patients who are not opioid tolerant may cause fatal respiratory depression [see Warnings and Precautions (5.2)].

Conversion from Oral Hydrocodone Formulations to HYSINGLA ER

Patients receiving other oral hydrocodone-containing formulations may be converted to HYSINGLA ER by administering the patient's total daily oral hydrocodone dose as HYSINGLA ER once daily.

Conversion from Fentanyl Transdermal System to HYSINGLA ER

Eighteen hours following the removal of the fentanyl transdermal system, HYSINGLA ER treatment can be initiated. For each 25 mcg/hr fentanyl transdermal system, a dose of HYSINGLA ER 20 mg every 24 hours represents a conservative initial dose. Follow the patient closely during conversion from fentanyl transdermal system to HYSINGLA ER, as there is limited experience with this conversion.

Conversion from Transdermal Buprenorphine to HYSINGLA ER

All patients receiving transdermal buprenorphine (≤ 20 mcg/hr) should initiate therapy with HYSINGLA ER 20 mg every 24 hours. Follow the patient closely during conversion from transdermal buprenorphine to HYSINGLA ER, as there is limited experience with this conversion.

Conversion from Other Opioid Analgesics to HYSINGLA ER

When HYSINGLA ER therapy is initiated, discontinue all other opioid analgesics other than those used on an as needed basis for breakthrough pain when appropriate.

There is inter-patient variability in the relative potency of opioid drugs and formulations. Therefore, a conservative approach is advised when determining the total daily dosage of HYSINGLA ER.

In a HYSINGLA ER clinical trial with an open-label titration period, patients were converted from their prior opioid to HYSINGLA ER using Table 1 as a guide for the initial HYSINGLA ER dose. To obtain the initial HYSINGLA ER dose, first use Table 1 to convert the prior oral opioids to a total hydrocodone daily dose and then reduce the calculated daily hydrocodone dose by 25% to account for interpatient variability in relative potency of different opioids.

Consider the following when using the information found in Table 1.

- This is not a table of equianalgesic doses.
- The conversion factors in this table are only for the conversion from one of the listed oral opioid analgesics to HYSINGLA ER.
- The table cannot be used to convert from HYSINGLA ER to another opioid. Doing so will result in an over-estimation of the dose of the new opioid and may result in fatal overdose

Table 1. Conversion factors to HYSINGLA ER (Not Equianalgesic Doses)
Opioid | Oral dose (mg) | Approximate oral conversion factor
Codeine | 133 | 0.15
Hydromorphone | 5 | 4
Methadone | 13.3 | 1.5
Morphine | 40 | 0.5
Oxycodone | 20 | 1
Oxymorphone | 10 | 2
Tramadol | 200 | 0.1

To calculate the estimated total hydrocodone daily dose using Table 1:

- For patients on a single opioid, sum the current total daily dose of the opioid and then multiply the total daily dose by the approximate oral conversion factor to calculate the approximate oral hydrocodone daily dose.
- For patients on a regimen of more than one opioid, calculate the approximate oral hydrocodone dose for each opioid and sum the totals to obtain the approximate oral hydrocodone daily dose.
- For patients on a regimen of fixed-ratio opioid/non-opioid analgesic products, use only the opioid component of these products in the conversion.
- Reduce the calculated daily oral hydrocodone dose by 25%

Always round the dose down, if necessary, to the nearest HYSINGLA ER tablet strength available and initiate therapy with that dose. If the converted HYSINGLA ER dose using Table 1 is less than 20 mg, initiate therapy with HYSINGLA ER 20 mg.

Example conversion from a single opioid to HYSINGLA ER:

For example, a total daily dose of oxycodone 50 mg would be converted to hydrocodone 50 mg based on the table above, and then multiplied by 0.75 (i.e., take a 25 % reduction) resulting in a dose of 37.5 mg hydrocodone. Round this down to the nearest dose strength available, HYSINGLA ER 30 mg, to initiate therapy.

Conversion from Methadone to HYSINGLA ER

Regular evaluation is of particular importance when converting from methadone to other opioid agonists. The ratio between methadone and other opioid agonists may vary widely as a function of previous dose exposure. Methadone has a long half-life and can accumulate in the plasma. Refer to Table 1 for more information.

2.4 Titration and Maintenance of Therapy

Individually titrate HYSINGLA ER to a dose that provides adequate analgesia and minimizes adverse reactions. Continually reevaluate patients receiving HYSINGLA ER to assess the maintenance of pain control, signs and symptoms of opioid withdrawal, and other relative incidence of adverse reactions, as well as to reassess for the development of addiction, abuse, or misuse [see Warnings and Precautions (5.1, 5.16)]. Frequent communication is important among the prescriber, other members of the healthcare team, the patient, and the caregiver/family during periods of changing analgesic requirements, including initial titration. During use of opioid therapy for an extended period of time, periodically reassess the continued need for the use of opioid analgesics.

Patients who experience breakthrough pain may require a dosage adjustment of HYSINGLA ER, or may need rescue medication with an appropriate dose of an immediate-release analgesic.

If the level of pain increases after dose stabilization, attempt to identify the source of increased pain before increasing the HYSINGLA ER dosage. If after increasing the dosage, unacceptable opioid-related adverse reactions are observed (including an increase in pain after a dosage increase), consider reducing the dosage [see Warnings and Precautions (5)]. Adjust the dosage to obtain an appropriate balance between management of pain and opioid-related adverse reactions. Adjust the dose of HYSINGLA ER in increments of 10 mg to 20 mg every 3 to 5 days as needed to achieve adequate analgesia.

2.5 Dosage Modifications in Patients with Severe Hepatic Impairment

Patients with severe hepatic impairment may have higher plasma concentrations of hydrocodone than those with normal function. Initiate therapy with one half the initial dose of HYSINGLA ER in these patients and regularly evaluate for respiratory depression, sedation, and hypotension [see Clinical Pharmacology (12.3)].

2.6 Dosage Modifications in Patients with Moderate to Severe Renal Impairment

Patients with moderate to severe renal impairment, and end-stage renal disease may have higher plasma concentrations than those with normal function. Initiate therapy with one half the initial dose of HYSINGLA ER in these patients and regularly evaluate for respiratory depression, sedation, and hypotension [see Clinical Pharmacology (12.3)].

2.7 Safe Reduction or Discontinuation of HYSINGLA ER

Do not rapidly reduce or abruptly discontinue HYSINGLA ER in patients who may be physically dependent on opioids. Rapid reduction or abrupt discontinuation of opioid analgesics in patients who are physically dependent on opioids has resulted in serious withdrawal symptoms, uncontrolled pain, and suicide. Rapid reduction or abrupt discontinuation has also been associated with attempts to find other sources of opioid analgesics, which may be confused with drug-seeking for abuse. Patients may also attempt to treat their pain or withdrawal symptoms with illicit opioids, such as heroin, and other substances.

When a decision has been made to decrease the dose or discontinue therapy in an opioid-dependent patient taking HYSINGLA ER, there are a variety of factors that should be considered, including the total daily dose opioid (including HYSINGLA ER) the patient has been taking, the duration of treatment, the type of pain being treated, and the physical and psychological attributes of the patient. It is important to ensure ongoing care of the patient and to agree on an appropriate tapering schedule and follow-up plan so that patient and provider goals and expectations are clear and realistic. When opioid analgesics are being discontinued due to a suspected substance use disorder, evaluate and treat the patient, or refer for evaluation and treatment of the substance use disorder. Treatment should include evidence-based approaches, such as medication assisted treatment of opioid use disorder. Complex patients with comorbid pain and substance use disorders may benefit from referral to a specialist.

There are no standard opioid tapering schedules that are suitable for all patients. Good clinical practice dictates a patient-specific plan to taper the dose of the opioid gradually. For patients on HYSINGLA ER who are physically opioid-dependent, initiate the taper by a small enough increment (e.g., no greater than 10% to 25% of the total daily dose) to avoid withdrawal symptoms, and proceed with dose-lowering at an interval of every 2 to 4 weeks. Patients who have been taking opioids for briefer periods of time may tolerate a more rapid taper.

It may be necessary to provide the patient with lower dosage strengths to accomplish a successful taper. Reassess the patient frequently to manage pain and withdrawal symptoms, should they emerge. Common withdrawal symptoms include restlessness, lacrimation, rhinorrhea, yawning, perspiration, chills, myalgia, and mydriasis. Other signs and symptoms also may develop, including irritability, anxiety, backache, joint pain, weakness, abdominal cramps, insomnia, nausea, anorexia, vomiting, diarrhea, or increased blood pressure, respiratory rate, or heart rate. If withdrawal symptoms arise, it may be necessary to pause the taper for a period of time or raise the dose of the opioid analgesic to the previous dose, and then proceed with a slower taper. In addition, evaluate patients for any changes in mood, emergence of suicidal thoughts, or use of other substances.

When managing patients taking opioid analgesics, particularly those who have been treated for an extended period of time, and/or with high doses for chronic pain, ensure that a multimodal approach to pain management, including mental health support (if needed), is in place prior to initiating an opioid analgesic taper. A multimodal approach to pain management may optimize the treatment of chronic pain, as well as assist with the successful tapering of the opioid analgesic [see Warnings and Precautions (5.16), Drug Abuse and Dependence (9.3)].

3 DOSAGE FORMS AND STRENGTHS

- 20 mg film-coated extended-release tablets (round, green-colored, bi-convex tablets printed with "HYD 20")
- 30 mg film-coated extended-release tablets (round, yellow-colored, bi-convex tablets printed with "HYD 30")
- 40 mg film-coated extended-release tablets (round, grey-colored, bi-convex tablets printed with "HYD 40")
- 60 mg film-coated extended-release tablets (round, beige-colored, bi-convex tablets printed with "HYD 60")
- 80 mg film-coated extended-release tablets (round, pink-colored, bi-convex tablets printed with "HYD 80")
- 100 mg film-coated extended-release tablets (round, blue-colored, bi-convex tablets printed with "HYD 100")
- 120 mg film-coated extended-release tablets (round, white-colored, bi-convex tablets printed with "HYD 120")

4 CONTRAINDICATIONS

HYSINGLA ER is contraindicated in patients with:

- Significant respiratory depression [see Warnings and Precautions (5.2)]
- Acute or severe bronchial asthma in an unmonitored setting or in the absence of resuscitative equipment [see Warnings and Precautions (5.8)]
- Known or suspected gastrointestinal obstruction, including paralytic ileus [see Warnings and Precautions (5.13, 5.14)]
- Hypersensitivity to hydrocodone or any component of HYSINGLA ER.

5 WARNINGS AND PRECAUTIONS

5.1 Addiction, Abuse, and Misuse

HYSINGLA ER contains hydrocodone, a Schedule II controlled substance. As an opioid, HYSINGLA ER exposes users to the risks of addiction, abuse, and misuse. Although the risk of addiction in any individual is unknown, it can occur in patients appropriately prescribed HYSINGLA ER. Addiction can occur at recommended doses and if the drug is misused or abused. The risk of opioid-related overdose or overdose-related death is increased with higher opioid doses, and this risk persists over the course of therapy. In postmarketing studies, addiction, abuse, misuse, and fatal and non-fatal opioid overdose were observed in patients with long-term opioid use [see Adverse Reactions (6.2)].

Assess each patient's risk for opioid addiction, abuse, or misuse prior to prescribing HYSINGLA ER, and reassess all patients receiving HYSINGLA ER for the development of these behaviors and conditions. Risks are increased in patients with a personal or family history of substance abuse (including drug or alcohol abuse or addiction) or mental illness (e.g., major depression). The potential for these risks should not, however, prevent the prescribing of HYSINGLA ER for the proper management of pain in any given patient. Patients at increased risk may be prescribed opioids such as HYSINGLA ER, but use in such patients necessitates intensive counseling about the risks and proper use of HYSINGLA ER along with frequent reevaluation for signs of addiction, abuse, and misuse. Consider recommending or prescribing an opioid overdose reversal agent [see Dosage and Administration (2.2), Warnings and Precautions (5.2)].

Abuse or misuse of HYSINGLA ER by crushing, chewing, snorting, or injecting the dissolved product will result in the uncontrolled delivery of the hydrocodone and can result in overdose and death [see Drug Abuse and Dependence (9.2), Overdosage (10)].

Opioids are sought for nonmedical use and are subject to diversion from legitimate prescribed use. Consider these risks when prescribing or dispensing HYSINGLA ER. Strategies to reduce these risks include prescribing the drug in the smallest appropriate quantity and advising the patient on careful storage of the drug during the course of treatment and the proper disposal of unused drug. Contact local state professional licensing board or state-controlled substances authority for information on how to prevent and detect abuse or diversion of this product.

5.2 Life-Threatening Respiratory Depression

Serious, life-threatening, or fatal respiratory depression has been reported with the use of opioids, even when used as recommended. Respiratory depression, if not immediately recognized and treated, may lead to respiratory arrest and death. Management of respiratory depression may include close observation, supportive measures, and use of opioid overdose reversal agents, depending on the patient's clinical status [see Overdosage (10)]. Carbon dioxide (CO2) retention from opioid-induced respiratory depression can exacerbate the sedating effects of opioids.

While serious, life-threatening, or fatal respiratory depression can occur at any time during the use of HYSINGLA ER, the risk is greatest during the initiation of therapy or following a dosage increase.

To reduce the risk of respiratory depression, proper dosing and titration of HYSINGLA ER are essential [see Dosage and Administration (2.1, 2.3)]. Overestimating the HYSINGLA ER dosage when converting patients from another opioid product can result in fatal overdose with the first dose.

Accidental ingestion of even one dose of HYSINGLA ER, especially by children, can result in respiratory depression and death due to an overdose of hydrocodone.

Educate patients and caregivers on how to recognize respiratory depression and emphasize the importance of calling 911 or getting emergency medical help right away in the event of a known or suspected overdose.

Opioids can cause sleep-related breathing disorders including central sleep apnea (CSA) and sleep-related hypoxemia. Opioid use increases the risk of CSA in a dose-dependent fashion. In patients who present with CSA, consider decreasing the opioid dosage using best practices for opioid taper [see Dosage and Administration (2.4)].

Patient Access to an Opioid Overdose Reversal Agent for the Emergency Treatment of Opioid Overdose:

Inform patients and caregivers about opioid overdose reversal agents (e.g., naloxone, nalmefene). Discuss the importance of having access to an opioid overdose reversal agent, especially if the patient has risk factors for overdose (e.g., concomitant use of CNS depressants, a history of opioid use disorder, or prior opioid overdose) or if there are household members (including children) or other close contacts at risk for accidental ingestion or opioid overdose. The presence of risk factors for overdose should not prevent the management of pain in any patient [Warnings and Precautions (5.1, 5.3)].

Discuss the options for obtaining an opioid overdose reversal agent (e.g., prescription, over-the-counter, or as part of a community-based program).

There are important differences among the opioid overdose reversal agents, such as route of administration, product strength, approved patient age range, and pharmacokinetics. Be familiar with these differences, as outlined in the approved labeling for those products, prior to recommending or prescribing such an agent.

Educate patients and caregivers on how to recognize respiratory depression, and how to use an opioid overdose reversal agent for the emergency treatment of opioid overdose. Emphasize the importance of calling 911 or getting emergency medical help, even if an opioid overdose reversal agent is administered [see Dosage and Administration (2.2), Warnings and Precautions (5.1, 5.3), Overdosage (10)].

5.3 Risks of Concomitant Use with Benzodiazepines or Other CNS Depressants

Profound sedation, respiratory depression, coma, and death may result from the concomitant use of HYSINGLA ER with benzodiazepines and/or other CNS depressants, including alcohol (e.g., non-benzodiazepine sedatives/hypnotics, anxiolytics, tranquilizers, muscle relaxants, general anesthetics, antipsychotics, gabapentinoids [gabapentin or pregabalin], and other opioids). Because of these risks, reserve concomitant prescribing of these drugs for use in patients for whom alternative treatment options are inadequate.

Observational studies have demonstrated that concomitant use of opioid analgesics and benzodiazepines increases the risk of drug-related mortality compared to use of opioid analgesics alone. Because of similar pharmacological properties, it is reasonable to expect similar risk with the concomitant use of other CNS depressant drugs with opioid analgesics [see Drug Interactions (7)].

If the decision is made to prescribe a benzodiazepine or other CNS depressant concomitantly with an opioid analgesic, prescribe the lowest effective dosages and minimum durations of concomitant use. In patients already receiving an opioid analgesic, prescribe a lower initial dose of the benzodiazepine or other CNS depressant than indicated in the absence of an opioid, and titrate based on clinical response. If an opioid analgesic is initiated in a patient already taking a benzodiazepine or other CNS depressant, prescribe a lower initial dose of the opioid analgesic, and titrate based on clinical response. Inform patients and caregivers of this potential interaction and educate them on the signs and symptoms of respiratory depression (including sedation).

If concomitant use is warranted, consider recommending or prescribing an opioid overdose reversal agent [see Dosage and Administration (2.2), Warnings and Precautions (5.2), Overdosage (10)].

Advise both patients and caregivers about the risks of respiratory depression and sedation when HYSINGLA ER is used with benzodiazepines or other CNS depressants (including alcohol and illicit drugs). Advise patients not to drive or operate heavy machinery until the effects of concomitant use of the benzodiazepine or other CNS depressant have been determined. Screen patients for risk of substance use disorders, including opioid abuse and misuse, and warn them of the risk for overdose and death associated with the use of additional CNS depressants including alcohol and illicit drugs [see Drug Interactions (7)].

5.4 Neonatal Opioid Withdrawal Syndrome

Use of HYSINGLA ER for an extended period of time during pregnancy can result in withdrawal in the neonate. Neonatal opioid withdrawal syndrome, unlike opioid withdrawal syndrome in adults, may be life-threatening if not recognized and treated, and requires management according to protocols developed by neonatology experts. Observe newborns for signs of neonatal opioid withdrawal syndrome and manage accordingly. Advise pregnant women using opioids for an extended period of time of the risk of neonatal opioid withdrawal syndrome and ensure that appropriate treatment will be available [see Use in Specific Populations (8.1)].

5.5 Opioid Analgesic Risk Evaluation and Mitigation Strategy (REMS)

To ensure that the benefits of opioid analgesics outweigh the risks of addiction, abuse, and misuse, the Food and Drug Administration (FDA) has required a Risk Evaluation and Mitigation Strategy (REMS) for these products. Under the requirements of the REMS, drug companies with approved opioid analgesic products must make REMS-compliant education programs available to healthcare providers. Healthcare providers are strongly encouraged to do all of the following:

- Complete a REMS-compliant education program offered by an accredited provider of continuing education (CE) or another education program that includes all the elements of the FDA Education Blueprint for Health Care Providers Involved in the Management or Support of Patients with Pain.
- Discuss the safe use, serious risks, and proper storage and disposal of opioid analgesics with patients and/or their caregivers every time these medicines are prescribed. The Patient Counseling Guide (PCG) can be obtained at this link:
  www.fda.gov/OpioidAnalgesicREMSPCG.
- Emphasize to patients and their caregivers the importance of reading the Medication Guide that they will receive from their pharmacist every time an opioid analgesic is dispensed to them.
- Consider using other tools to improve patient, household, and community safety, such as patient- prescriber agreements that reinforce patient-prescriber responsibilities.

To obtain further information on the opioid analgesic REMS and for a list of accredited REMS CME/CE, call 1-800-503-0784, or log on to www.opioidanalgesicrems.com. The FDA Blueprint can be found at www.fda.gov/OpioidAnalgesicREMSBlueprint

5.6 Risks of Concomitant Use or Discontinuation of Cytochrome P450 3A4 Inhibitors and Inducers

Concomitant use of HYSINGLA ER with a CYP3A4 inhibitor, such as macrolide antibiotics (e.g., erythromycin), azole-antifungal agents (e.g., ketoconazole), and protease inhibitors (e.g., ritonavir), may increase plasma concentrations of hydrocodone and prolong opioid adverse reactions, which may cause potentially fatal respiratory depression [see Warnings and Precautions (5.2)], particularly when an inhibitor is added after a stable dose of HYSINGLA ER is achieved. Similarly, discontinuation of a CYP3A4 inducer, such as rifampin, carbamazepine, and phenytoin, in HYSINGLA ER treated patients may increase hydrocodone plasma concentrations and prolong opioid adverse reactions. When using HYSINGLA ER with CYP3A4 inhibitors or discontinuing CYP3A4 inducers in HYSINGLA ER-treated patients, evaluate patients at frequent intervals and consider dosage reduction of HYSINGLA ER until stable drug effects are achieved [see Drug Interactions (7)].

Concomitant use of HYSINGLA ER with CYP3A4 inducers or discontinuation of an CYP3A4 inhibitor could decrease hydrocodone plasma concentrations, decrease opioid efficacy or, possibly, lead to a withdrawal syndrome in a patient who had developed physical dependence to hydrocodone. When using HYSINGLA ER with CYP3A4 inducers or discontinuing CYP3A4 inhibitors, monitor patients closely at frequent intervals and consider increasing the opioid dosage if needed to maintain adequate analgesia or if symptoms of opioid withdrawal occur [see Drug Interactions (7)].

5.7 Opioid-Induced Hyperalgesia and Allodynia

Opioid-Induced Hyperalgesia (OIH) occurs when an opioid analgesic paradoxically causes an increase in pain, or an increase in sensitivity to pain. This condition differs from tolerance, which is the need for increasing doses of opioids to maintain a defined effect [see Dependence (9.3)]. Symptoms of OIH include (but may not be limited to) increased levels of pain upon opioid dosage increase, decreased levels of pain upon opioid dosage decrease, or pain from ordinarily non-painful stimuli (allodynia). These symptoms may suggest OIH only if there is no evidence of underlying disease progression, opioid tolerance, opioid withdrawal, or addictive behavior.

Cases of OIH have been reported, both with short-term and longer-term use of opioid analgesics. Though the mechanism of OIH is not fully understood, multiple biochemical pathways have been implicated. Medical literature suggests a strong biologic plausibility between opioid analgesics and OIH and allodynia. If a patient is suspected to be experiencing OIH, carefully consider appropriately decreasing the dose of the current opioid analgesic, or opioid rotation (safely switching the patient to a different opioid moiety) [see Dosage and Administration (2.7), Warnings and Precautions (5.16)].

5.8 Life-Threatening Respiratory Depression in Patients with Chronic Pulmonary Disease or in Elderly, Cachectic, or Debilitated Patients

The use of HYSINGLA ER in patients with acute or severe bronchial asthma in an unmonitored setting or in the absence of resuscitative equipment is contraindicated.

Patients with Chronic Pulmonary Disease: HYSINGLA ER-treated patients with significant chronic obstructive pulmonary disease or cor pulmonale, and those with a substantially decreased respiratory reserve, hypoxia, hypercapnia, or pre-existing respiratory depression are at increased risk of decreased respiratory drive including apnea, even at recommended dosages of HYSINGLA ER [see Warnings and Precautions (5.2)].

Elderly, Cachectic, or Debilitated Patients: Life-threatening respiratory depression is more likely to occur in elderly, cachectic, or debilitated patients because they may have altered pharmacokinetics or altered clearance compared to younger, healthier patients [see Warnings and Precautions (5.2)].

Regularly evaluate patients, particularly when initiating and titrating HYSINGLA ER and when HYSINGLA ER is given concomitantly with other drugs that depress respiration [see Warnings and Precautions (5.2, 5.3), Drug Interactions (7)]. Alternatively, consider the use of non-opioid analgesics in these patients.

5.9 Adrenal Insufficiency

Cases of adrenal insufficiency have been reported with opioid use, more often following greater than one month of use. Presentation of adrenal insufficiency may include non-specific symptoms and signs including nausea, vomiting, anorexia, fatigue, weakness, dizziness, and low blood pressure. If adrenal insufficiency is suspected, confirm the diagnosis with diagnostic testing as soon as possible. If adrenal insufficiency is diagnosed, treat with physiologic replacement doses of corticosteroids. Wean the patient off of the opioid to allow adrenal function to recover and continue corticosteroid treatment until adrenal function recovers. Other opioids may be tried as some cases reported use of a different opioid without recurrence of adrenal insufficiency. The information available does not identify any particular opioids as being more likely to be associated with adrenal insufficiency.

5.10 Severe Hypotension

HYSINGLA ER may cause severe hypotension including orthostatic hypotension and syncope in ambulatory patients. There is an increased risk in patients whose ability to maintain blood pressure has already been compromised by a reduced blood volume, or after concurrent administration of certain CNS depressant drugs (e.g., phenothiazines or general anesthetics) [see Drug Interactions (7)]. Regularly evaluate these patients for signs of hypotension after initiating or titrating the dosage of HYSINGLA ER. In patients with circulatory shock, HYSINGLA ER may cause vasodilation that can further reduce cardiac output and blood pressure. Avoid the use of HYSINGLA ER in patients with circulatory shock.

5.11 QTc Interval Prolongation

QTc prolongation has been observed with HYSINGLA ER following daily doses of 160 mg [see Clinical Pharmacology (12.2)]. This observation should be considered in making clinical decisions regarding patient monitoring when prescribing HYSINGLA ER in patients with congestive heart failure, bradyarrhythmias, electrolyte abnormalities, or who are taking medications that are known to prolong the QTc interval.

HYSINGLA ER should be avoided in patients with congenital long QT syndrome. In patients who develop QTc prolongation, consider reducing the dose by 33 – 50%, or changing to an alternate analgesic.

5.12 Risks of Use in Patients with Increased Intracranial Pressure, Brain Tumors, Head Injury, or Impaired Consciousness

In patients who may be susceptible to the intracranial effects of CO2 retention (e.g., those with evidence of increased intracranial pressure or brain tumors), HYSINGLA ER may reduce respiratory drive, and the resultant CO2 retention can further increase intracranial pressure. Monitor such patients for signs of sedation and respiratory depression, particularly when initiating therapy with HYSINGLA ER.

Opioids may also obscure the clinical course in a patient with a head injury. Avoid the use of HYSINGLA ER in patients with impaired consciousness or coma.

5.13 Gastrointestinal Obstruction, Dysphagia, and Choking

In the clinical studies with specific instructions to take HYSINGLA ER with adequate water to swallow the tablet, 11 out of 2476 subjects reported difficulty swallowing HYSINGLA ER. These reports included esophageal obstruction, dysphagia, and choking, one of which had required medical intervention to remove the tablet [see Adverse Reactions (6)].

Instruct patients not to pre-soak, lick, or otherwise wet HYSINGLA ER tablets prior to placing in the mouth, and to take one tablet at a time with enough water to ensure complete swallowing immediately after placing in the mouth.

Patients with underlying gastrointestinal disorders such as esophageal cancer or colon cancer with a small gastrointestinal lumen are at greater risk of developing these complications. Consider use of an alternative analgesic in patients who have difficulty swallowing and patients at risk for underlying gastrointestinal disorders resulting in a small gastrointestinal lumen.

Pediatric patients may be at increased risk of esophageal obstruction, dysphagia, and choking because of a smaller gastrointestinal lumen if they ingest HYSINGLA ER [see Use in Specific Populations (8.4)].

5.14 Risks of Gastrointestinal Complications

HYSINGLA ER is contraindicated in patients with known or suspected gastrointestinal obstruction, including paralytic ileus.

The hydrocodone in HYSINGLA ER may cause spasm of the sphincter of Oddi. Opioids may cause increases in serum amylase. Regularly evaluate patients with biliary tract disease, including acute pancreatitis, for worsening symptoms.

Cases of opioid-induced esophageal dysfunction (OIED) have been reported in patients taking opioids. The risk of OIED may increase as the dose and/or duration of opioids increases. Regularly evaluate patients for signs and symptoms of OIED (e.g., dysphagia, regurgitation, non-cardiac chest pain) and, if necessary, adjust opioid therapy as clinically appropriate [see Clinical Pharmacology (12.2)].

5.15 Increased Risk of Seizures in Patients with Seizure Disorders

The hydrocodone in HYSINGLA ER may increase the frequency of seizures in patients with seizure disorders, and may increase the risk of seizures occurring in other clinical settings associated with seizures. Regularly evaluate patients with a history of seizure disorders for worsened seizure control during HYSINGLA ER therapy.

5.16 Withdrawal

Do not rapidly reduce or abruptly discontinue HYSINGLA ER in a patient physically dependent on opioids. When discontinuing HYSINGLA ER in a physically dependent patient, gradually taper the dosage. Rapid tapering of hydrocodone in a patient physically dependent on opioids may lead to a withdrawal syndrome and return of pain [see Dosage and Administration (2.7), Drug Abuse and Dependence (9.3)].

Additionally, avoid the use of mixed agonist/antagonist analgesics (e.g., pentazocine, nalbuphine, and butorphanol) or partial agonist (e.g., buprenorphine) analgesics in patients who are receiving a full opioid agonist analgesic, including HYSINGLA ER. In these patients, mixed agonist/antagonist and partial agonist analgesics may reduce the analgesic effect and/or may precipitate withdrawal symptoms [see Drug Interactions (7)].

5.17 Risks of Driving and Operating Machinery

HYSINGLA ER may impair the mental and physical abilities needed to perform potentially hazardous activities such as driving a car or operating machinery. Peak blood levels of hydrocodone may occur 14 – 16 hours (range 6 – 30 hours) after initial dosing of HYSINGLA ER tablet administration. Blood levels of hydrocodone, in some patients, may be high at the end of 24 hours after repeated-dose administration. Warn patients not to drive or operate dangerous machinery unless they are tolerant to the effects of HYSINGLA ER and know how they will react to the medication.

6 ADVERSE REACTIONS

The following serious adverse reactions are described elsewhere in the labeling:

- Addiction, Abuse, and Misuse [see Warnings and Precautions (5.1)]
- Life-Threatening Respiratory Depression [see Warnings and Precautions (5.2)]
- Interactions with Benzodiazepine or Other CNS Depressants [see Warnings and Precautions (5.3)]
- Neonatal Opioid Withdrawal Syndrome [see Warnings and Precautions (5.4)]
- Opioid-Induced Hyperalgesia and Allodynia [see Warnings and Precautions (5.7)]
- Adrenal Insufficiency [see Warnings and Precautions (5.9)]
- Severe Hypotension [see Warnings and Precautions (5.10)]
- Gastrointestinal Adverse Reactions [see Warnings and Precautions (5.13, 5.14)]
- Seizures [see Warnings and Precautions (5.15)]
- Withdrawal [see Warnings and Precautions (5.16)]

6.1 Clinical Trial Experience

Because clinical trials are conducted under widely varying conditions, adverse reaction rates observed in the clinical trials of a drug cannot be directly compared to rates in the clinical trials of another drug and may not reflect the rates observed in practice.

A total of 1,827 patients were treated with HYSINGLA ER in controlled and open-label chronic pain clinical trials. Five hundred patients were treated for 6 months and 364 patients were treated for 12 months. The clinical trial population consisted of patients who were not opioid tolerant and opioid-experienced patients with persistent moderate to severe chronic pain.

The common adverse reactions (≥2%) reported by patients in clinical trials comparing HYSINGLA ER (20-120 mg/day) with placebo are shown in Table 2 below:

Table 2: Adverse Reactions Reported in ≥2% of Patients during the Open-Label Titration Period and Double-Blind Treatment Period: Patients Who Were Not Opioid Tolerant and Opioid-Experienced Patients
 |  | Open-label Titration Period | Double-blind Treatment Period
MedDRA Preferred Term |  | (N=905) (%) | Placebo (N=292) (%) | HYSINGLA ER (N=296) (%)
Nausea |  | 16 | 5 | 8
Constipation |  | 9 | 2 | 3
Vomiting |  | 7 | 3 | 6
Dizziness |  | 7 | 2 | 3
Headache |  | 7 | 2 | 2
Somnolence |  | 5 | 1 | 1
Fatigue |  | 4 | 1 | 1
Pruritus |  | 3 | <1 | 0
Tinnitus |  | 2 | 1 | 2
Insomnia |  | 2 | 2 | 3
Decreased appetite |  | 1 | 1 | 2
Influenza |  | 1 | 1 | 3

The adverse reactions seen in controlled and open-label chronic pain studies are presented below in the following manner: most common (≥5%), common (≥1% to <5%), and less common (<1%).

The most common adverse reactions (≥5%) reported by patients treated with HYSINGLA ER in the chronic pain clinical trials were constipation, nausea, vomiting, fatigue, upper respiratory tract infection, dizziness, headache, somnolence.

The common (≥1% to <5%) adverse events reported by patients treated with HYSINGLA ER in the chronic pain clinical trials organized by MedDRA (Medical Dictionary for Regulatory Activities) System Organ Class were:

Ear and labyrinth disorders | tinnitus
Gastrointestinal disorders | abdominal pain, abdominal pain upper, diarrhea, dry mouth, dyspepsia, gastroesophageal reflux disease
General disorders and administration site conditions | chest pain, chills, edema peripheral, pain, pyrexia
Infections and infestations | bronchitis, gastroenteritis, gastroenteritis viral, influenza, nasopharyngitis, sinusitis, urinary tract infection
Injury, poisoning and procedural complications | fall, muscle strain
Metabolism and nutrition disorders | decreased appetite
Musculoskeletal and connective tissue disorders | arthralgia, back pain, muscle spasms, musculoskeletal pain, myalgia, pain in extremity
Nervous system disorders | lethargy, migraine, sedation
Psychiatric disorders | anxiety, depression, insomnia
Respiratory, thoracic and mediastinal disorders | cough, nasal congestion, oropharyngeal pain
Skin and subcutaneous tissue disorders | hyperhidrosis, pruritus, rash
Vascular disorders | hot flush, hypertension

Other less common adverse reactions that were seen in <1% of the patients in the HYSINGLA ER chronic pain clinical trials include the following in alphabetical order: abdominal discomfort, abdominal distention, agitation, asthenia, choking, confusional state, depressed mood, drug hypersensitivity, drug withdrawal syndrome, dysphagia, dyspnea, esophageal obstruction, flushing, hypogonadism, hypotension, hypoxia, irritability, libido decreased, malaise, mental impairment, mood altered, muscle twitching, edema, orthostatic hypotension, palpitations, presyncope, retching, syncope, thinking abnormal, thirst, tremor, and urinary retention.

6.2 Postmarketing Experience

The following adverse reactions have been identified during post approval use of hydrocodone. Because these reactions are reported voluntarily from a population of uncertain size, it is not always possible to reliably estimate their frequency or establish a causal relationship to drug exposure.

Serotonin syndrome: Cases of serotonin syndrome, a potentially life-threatening condition, have been reported during concomitant use of opioids with serotonergic drugs.

Adrenal insufficiency: Cases of adrenal insufficiency have been reported with opioid use, more often following greater than one month of use.

Anaphylaxis: Anaphylaxis has been reported with ingredients contained in HYSINGLA ER.

Androgen deficiency: Cases of androgen deficiency have occurred with use of opioids for an extended period of time [see Clinical Pharmacology (12.2)].

Hyperalgesia and Allodynia: Cases of hyperalgesia and allodynia have been reported with opioid therapy of any duration [see Warnings and Precautions (5.7)].

Hypoglycemia: Cases of hypoglycemia have been reported in patients taking opioids. Most reports were in patients with at least one predisposing risk factor (e.g., diabetes).

Opioid-induced esophageal dysfunction (OIED): Cases of OIED have been reported in patients taking opioids and may occur more frequently in patients taking higher doses of opioids, and/or in patients taking opioids longer term [see Warnings and Precautions (5.14)].

Adverse Reactions from Observational Studies

A prospective, observational cohort study estimated the risks of addiction, abuse, and misuse in patients initiating long-term use of Schedule II opioid analgesics between 2017 and 2021. Study participants included in one or more analyses had been enrolled in selected insurance plans or health systems for at least one year, were free of at least one outcome at baseline, completed a minimum number of follow-up assessments, and either: 1) filled multiple extended-release/long-acting opioid analgesic prescriptions during a 90-day period (n=978); or 2) filled any Schedule II opioid analgesic prescriptions covering at least 70 of 90 days (n=1,244). Those included also had no dispensing of the qualifying opioids in the previous 6 months.

Over 12 months:

- approximately 1% to 6% of participants across the two cohorts newly met criteria for addiction, as assessed with two validated interview- based measures of moderate-to-severe opioid use disorder based on Diagnostic and Statistical Manual of Mental Disorders, Fifth Edition (DSM-5) criteria, and
- approximately 9% and 22% of participants across the two cohorts newly met criteria for prescription opioid abuse and misuse [defined in Drug Abuse and Dependence (9.2)], respectively, as measured with a validated self-reported instrument.

A retrospective, observational cohort study estimated the risk of opioid- involved overdose or opioid overdose-related death in patients with new long-term use of Schedule II opioid analgesics from 2006 through 2016 (n=220,249). Included patients had been enrolled in either one of two commercial insurance programs, one managed care program, or one Medicaid program for at least 9 months. New long-term use was defined as having Schedule II opioid analgesic prescriptions covering at least 70 days' supply over the 3 months prior to study entry and none during the preceding 6 months. Patients were excluded if they had an opioid-involved overdose in the 9 months prior to study entry. Overdose was measured using a validated medical code-based algorithm with linkage to the National Death Index database. The 5-year cumulative incidence estimates for opioid-involved overdose or opioid overdose-related death ranged from approximately 1.5% to 4% across study sites, counting only the first event during follow-up. Approximately 17% of first opioid overdoses observed over the entire study period (5-11 years, depending on the study site) were fatal. Higher baseline opioid dose was the strongest and most consistent predictor of opioid-involved overdose or opioid overdose-related death. Study exclusion criteria may have selected patients at lower risk of overdose, and substantial loss to follow-up (approximately 80%) also may have biased estimates.

The risk estimates from the studies described above may not be generalizable to all patients receiving opioid analgesics, such as those with exposures shorter or longer than the duration evaluated in the studies.

7 DRUG INTERACTIONS

Table 3 includes clinically significant drug interactions with HYSINGLA ER.

Table 3: Clinically Significant Drug Interactions with HYSINGLA ER
Inhibitors of CYP3A4
Clinical Impact: | The concomitant use of HYSINGLA ER and CYP3A4 inhibitors can increase the plasma concentration of hydrocodone, resulting in increased or prolonged opioid effects. These effects could be more pronounced with concomitant use of HYSINGLA ER and CYP3A4 inhibitors, particularly when an inhibitor is added after a stable dose of HYSINGLA ER is achieved [see Warnings and Precautions (5.6)]. After stopping a CYP3A4 inhibitor, as the effects of the inhibitor decline, the hydrocodone plasma concentration will decrease [see Clinical Pharmacology (12.3)], resulting in decreased opioid efficacy or a withdrawal syndrome in patients who had developed physical dependence to hydrocodone.
Intervention: | If concomitant use is necessary, consider dosage reduction of HYSINGLA ER until stable drug effects are achieved. Evaluate patients at frequent intervals for respiratory depression and sedation. If a CYP3A4 inhibitor is discontinued, consider increasing the HYSINGLA ER dosage until stable drug effects are achieved. Assess for signs of opioid withdrawal.
Examples | Macrolide antibiotics (e.g., erythromycin), azole-antifungal agents (e.g., ketoconazole), protease inhibitors (e.g., ritonavir).
CYP3A4 Inducers
Clinical Impact: | The concomitant use of HYSINGLA ER and CYP3A4 inducers can decrease the plasma concentration of hydrocodone [see Clinical Pharmacology (12.3)], resulting in decreased efficacy or onset of a withdrawal syndrome in patients who have developed physical dependence to hydrocodone [see Warnings and Precautions (5.6)]. After stopping a CYP3A4 inducer, as the effects of the inducer decline, the hydrocodone plasma concentration will increase [see Clinical Pharmacology (12.3)], which could increase or prolong both the therapeutic effects and adverse reactions, and may cause serious respiratory depression.
Intervention: | If concomitant use is necessary, consider increasing the HYSINGLA ER dosage until stable drug effects are achieved. Evaluate for signs of opioid withdrawal. If a CYP3A4 inducer is discontinued, consider HYSINGLA ER dosage reduction and evaluate patients at frequent intervals for signs of respiratory depression and sedation.
Examples: | Rifampin, carbamazepine, phenytoin
Benzodiazepines and Other Central Nervous System (CNS) Depressants
Clinical Impact: | Due to additive pharmacologic effect, the concomitant use of benzodiazepines or other CNS depressants, including alcohol, can increase the risk of hypotension, respiratory depression, profound sedation, coma, and death [see Warnings and Precautions (5.3)].
Intervention: | Reserve concomitant prescribing of these drugs for use in patients for whom alternative treatment options are inadequate. Limit dosages and durations to the minimum required. Inform patients and caregivers of this potential interaction and educate them on the signs and symptoms of respiratory depression (including sedation). If concomitant use is warranted, consider recommending or prescribing an opioid overdose reversal agent [see Dosage and Administration (2.2), Warnings and Precautions (5.1, 5.2, 5.3)].
Examples: | Benzodiazepines and other sedatives/hypnotics, anxiolytics, tranquilizers, muscle relaxants, general anesthetics, antipsychotics, gabapentinoids (gabapentin or pregabalin), other opioids, alcohol.
Serotonergic Drugs
Clinical Impact: | The concomitant use of opioids with other drugs that affect the serotonergic neurotransmitter system has resulted in serotonin syndrome.
Intervention: | If concomitant use is warranted, frequently evaluate the patient, particularly during treatment initiation and dose adjustment. Discontinue HYSINGLA ER if serotonin syndrome is suspected.
Examples: | Selective serotonin reuptake inhibitors (SSRIs), serotonin and norepinephrine reuptake inhibitors (SNRIs), tricyclic antidepressants (TCAs), triptans, 5-HT3 receptor antagonists, drugs that affect the serotonin neurotransmitter system (e.g., mirtazapine, trazodone, tramadol), certain muscle relaxants (i.e., cyclobenzaprine, metaxalone), monoamine oxidase inhibitors (those intended to treat psychiatric disorders and also others, such as linezolid and intravenous methylene blue).
Monoamine Oxidase Inhibitors (MAOIs)
Clinical Impact: | MAOI interactions with opioids may manifest as serotonin syndrome or opioid toxicity (e.g., respiratory depression, coma) [see Warnings and Precautions (5.3)].
Intervention: | The use of HYSINGLA ER is not recommended for patients taking MAOIs or within 14 days of stopping such treatment.
Examples: | Phenelzine, tranylcypromine, linezolid
Mixed Agonist/Antagonist and Partial Agonist Opioid Analgesics
Clinical Impact: | May reduce the analgesic effect of HYSINGLA ER and/or precipitate withdrawal symptoms.
Intervention: | Avoid concomitant use.
Examples: | butorphanol, nalbuphine, pentazocine, buprenorphine
Muscle Relaxants
Clinical Impact: | Hydrocodone may enhance the neuromuscular blocking action of skeletal muscle relaxants and produce an increased degree of respiratory depression.
Intervention: | Because respiratory depression may be greater than otherwise expected, decrease the dosage of HYSINGLA ER and/or the muscle relaxant as necessary. Due to the risk of respiratory depression with concomitant use of skeletal muscle relaxants and opioids, consider recommending or prescribing an opioid overdose reversal agent [see Dosage and Administration (2.2), Warnings and Precautions (5.2, 5.3)].
Example: | Cyclobenzaprine, metaxalone
Diuretics
Clinical Impact: | Opioids can reduce the efficacy of diuretics by inducing the release of antidiuretic hormone.
Intervention: | Evaluate patients for signs of diminished diuresis and/or effects on blood pressure and increase the dosage of the diuretic as needed.
Anticholinergic Drugs
Clinical Impact: | The concomitant use of anticholinergic drugs may increase risk of urinary retention and/or severe constipation, which may lead to paralytic ileus.
Intervention: | Evaluate patients for signs of urinary retention or reduced gastric motility when HYSINGLA ER is used concomitantly with anticholinergic drugs.
Strong Laxatives
Clinical Impact: | Concomitant use of HYSINGLA ER with strong laxatives that rapidly increase gastrointestinal motility, may decrease hydrocodone absorption and result in decreased hydrocodone plasma levels.
Intervention: | If HYSINGLA ER is used in these patients, regularly evaluate for the development of adverse events as well as changing analgesic requirements.
Example: | lactulose

8 USE IN SPECIFIC POPULATIONS

8.1 Pregnancy

Risk Summary

Use of opioid analgesics for an extended period of time during pregnancy may cause neonatal opioid withdrawal syndrome [see Warnings and Precautions (5.4)]. Available data with HYSINGLA ER in pregnant women are insufficient to inform a drug-associated risk for major birth defects and miscarriage. In animal reproduction studies with hydrocodone in rats and rabbits no embryotoxicity or teratogenicity was observed. However, reduced pup survival rates, reduced fetal/pup body weights, and delayed ossification were observed at doses causing maternal toxicity. In all of the studies conducted, the exposures in animals were less than the human exposure [see Data].

The background risk of major birth defects and miscarriage for the indicated population is unknown. All pregnancies have a background risk of birth defect, loss, or other adverse outcomes. In the U.S. general population, the estimated background risk of major birth defects and miscarriage in clinically recognized pregnancies is 2 to 4% and 15 to 20%, respectively.

Clinical Considerations

Fetal/neonatal adverse reactions

Use of opioid analgesics for extended period of time during pregnancy for medical or nonmedical purposes can result in physical dependence in the neonate and neonatal opioid withdrawal syndrome shortly after birth. Neonatal opioid withdrawal syndrome presents as irritability, hyperactivity and abnormal sleep pattern, high pitched cry, tremor, vomiting, diarrhea, and failure to gain weight. The onset, duration, and severity of neonatal opioid withdrawal syndrome vary based on the specific opioid used, duration of use, timing and amount of last maternal use, and rate of elimination of the drug by the newborn. Observe newborns for symptoms of neonatal opioid withdrawal syndrome and manage accordingly [see Warnings and Precautions (5.4)].

Labor and Delivery

Opioids cross the placenta and may produce respiratory depression and psycho-physiologic effects in neonates. An opioid overdose reversal agent, such as naloxone or nalmefene, must be available for reversal of opioid-induced respiratory depression in the neonate. HYSINGLA ER is not recommended for use in pregnant women during or immediately prior to labor, when use of shorter-acting analgesics or other analgesic techniques are more appropriate. Opioid analgesics, including HYSINGLA ER, can prolong labor through actions which temporarily reduce the strength, duration, and frequency of uterine contractions. However, this effect is not consistent and may be offset by an increased rate of cervical dilation, which tends to shorten labor. Monitor neonates exposed to opioid analgesics during labor for signs of excess sedation and respiratory depression.

Data

Animal Data

No evidence of embryotoxicity or teratogenicity was observed after oral administration of hydrocodone throughout the period of organogenesis in rats and rabbits at doses up to 30 mg/kg/day (approximately 0.1 and 0.3 times, respectively, the human hydrocodone dose of 120 mg/day based on AUC exposure comparisons). However, in these studies, reduced fetal body weights and delayed ossification were observed in rat at 30 mg/kg/day and reduced fetal body weights were observed in rabbits at 30 mg/kg/day (approximately 0.1 and 0.3 times, respectively, the human hydrocodone dose of 120 mg/day based on AUC exposure comparisons). In a pre- and post-natal development study pregnant rats were administered oral hydrocodone throughout the period of gestation and lactation. At a dose of 30 mg/kg/day decreased pup viability, pup survival indices, litter size and pup body weight were observed. This dose is approximately 0.1 times the human hydrocodone dose of 120 mg/day based on AUC exposure comparisons.

8.2 Lactation

Risk Summary

Hydrocodone is present in human milk. A published lactation study reports variable concentrations of hydrocodone and hydromorphone (an active metabolite) in breast milk with administration of immediate-release hydrocodone to nursing mothers in the early post-partum period. This lactation study did not assess breastfed infants for potential adverse drug reactions. Lactation studies have not been conducted with HYSINGLA, and no information is available on the effects of the drug on the breastfed infant or the effects of the drug on milk production. Because of the potential for serious adverse reactions, including excess sedation and respiratory depression in a breastfed infant, advise patients that breastfeeding is not recommended during treatment with HYSINGLA ER.

Clinical Considerations

Monitor infants exposed to HYSINGLA ER through breast milk for excess sedation and respiratory depression. Withdrawal symptoms can occur in breastfed infants when maternal administration of an opioid analgesic is stopped, or when breastfeeding is stopped.

8.3 Females and Males of Reproductive Potential

Infertility

Use of opioids for an extended period of time may cause reduced fertility in females and males of reproductive potential. It is not known whether these effects on fertility are reversible [see Adverse Reactions (6.2), Clinical Pharmacology (12.2), Nonclinical Toxicology (13.1)].

8.4 Pediatric Use

The safety and effectiveness of HYSINGLA ER in pediatric patients have not been established.

HYSINGLA ER gradually forms a viscous hydrogel (i.e., a gelatinous mass) when exposed to water or other fluids. Pediatric patients may be at increased risk of esophageal obstruction, dysphagia, and choking because of a smaller gastrointestinal lumen if they ingest HYSINGLA ER [see Warnings and Precautions (5.13)]

8.5 Geriatric Use

In a controlled pharmacokinetic study, elderly subjects (greater than 65 years) compared to young adults had similar plasma concentrations of hydrocodone [see Clinical Pharmacology (12.3)]. Of the 1827 subjects exposed to HYSINGLA ER in the pooled chronic pain studies, 241 (13%) were age 65 and older (including those age 75 and older), while 42 (2%) were age 75 and older. In clinical trials with appropriate initiation of therapy and dose titration, no untoward or unexpected adverse reactions were seen in the elderly patients who received HYSINGLA ER.

In general, use caution when selecting a dosage for an elderly patient, usually starting at the low end of the dosing range, reflecting the greater frequency of decreased hepatic, renal, or cardiac function and of concomitant disease or other drug therapy.

Respiratory depression is the chief risk for elderly patients treated with opioids, and has occurred after large initial doses were administered to patients who were not opioid-tolerant or when opioids were co-administered with other agents that depress respiration. Titrate the dosage of HYSINGLA ER slowly in geriatric patients and frequently reevaluate the patient for signs of central nervous system and respiratory depression [see Warnings and Precautions (5.8)].

Hydrocodone is known to be substantially excreted by the kidney, and the risk of adverse reactions to this drug may be greater in patients with impaired renal function. Because elderly patients are more likely to have decreased renal function, care should be taken in dose selection, and it may be useful to regularly evaluate renal function.

8.6 Hepatic Impairment

No adjustment in starting dose with HYSINGLA ER is required in patients with mild or moderate hepatic impairment. Patients with severe hepatic impairment may have higher plasma concentrations than those with normal hepatic function [see Clinical Pharmacology (12.3)]. Therefore, a dosage reduction is recommended for these patients [see Dosage and Administration (2.5)]. Regularly evaluate closely for respiratory depression, sedation, and hypotension.

8.7 Renal Impairment

No dose adjustment is needed in patients with mild renal impairment. Patients with moderate or severe renal impairment or end stage renal disease have higher plasma concentrations than those with normal renal function [see Clinical Pharmacology (12.3)]. Therefore, a dosage reduction is recommended for these patients [see Dosage and Administration (2.6)]. Regularly evaluate closely for respiratory depression, sedation, and hypotension.

9 DRUG ABUSE AND DEPENDENCE

9.1 Controlled Substance

HYSINGLA ER contains hydrocodone bitartrate, a Schedule II controlled substance.

9.2 Abuse

HYSINGLA ER contains hydrocodone, a substance with high potential for misuse and abuse, which can lead to the development of substance use disorder, including addiction [see Warnings and Precautions (5.1)].

Misuse is the intentional use, for therapeutic purposes, of a drug by an individual in a way other than prescribed by a healthcare provider or for whom it was not prescribed.

Abuse is the intentional, non-therapeutic use of a drug, even once, for its desirable psychological or physiological effects.

Drug addiction is a cluster of behavioral, cognitive, and physiological phenomena that may include a strong desire to take the drug, difficulties in controlling drug use (e.g., continuing drug use despite harmful consequences, giving a higher priority to drug use than other activities and obligations), and possible tolerance or physical dependence.

Misuse and abuse of HYSINGLA ER increases risk of overdose, which may lead to central nervous system and respiratory depression, hypotension, seizures, and death. The risk is increased with concurrent abuse of HYSINGLA ER with alcohol and other CNS depressants. Abuse of and addiction to opioids in some individuals may not be accompanied by concurrent tolerance and symptoms of physical dependence. In addition, abuse of opioids can occur in the absence of addiction.

All patients treated with opioids require careful and frequent reevaluation for signs of misuse, abuse, and addiction, because use of opioid analgesic products carries the risk of addiction even under appropriate medical use. Patients at high risk of HYSINGLA ER abuse include those with a history of prolonged use of any opioid, including products containing hydrocodone, those with a history of drug or alcohol abuse, or those who use HYSINGLA ER in combination with other abused drugs.

"Drug-seeking" behavior is very common in persons with substance use disorders. Drug seeking tactics include emergency calls or visits near the end of office hours, refusal to undergo appropriate examination, testing, or referral, repeated "loss" of prescriptions, tampering with prescriptions, and reluctance to provide prior medical records or contact information for other treating healthcare provider(s). "Doctor shopping" (visiting multiple prescribers to obtain additional prescriptions) is common among people who abuse drugs and people with substance use disorder. Preoccupation with achieving adequate pain relief can be appropriate behavior in a patient with inadequate pain control.

HYSINGLA ER, like other opioids, can be diverted for nonmedical use into illicit channels of distribution. Careful record-keeping of prescribing information, including quantity, frequency, and renewal requests, as required by state and federal law, is strongly advised.

Proper assessment of the patient, proper prescribing practices, periodic reevaluation of therapy, and proper dispensing and storage are appropriate measures that help to limit abuse of opioid drugs.

Risks Specific to Abuse of HYSINGLA ER

Abuse of HYSINGLA ER poses a risk of overdose and death. This risk is increased with concurrent use of HYSINGLA ER with alcohol and/or other CNS depressants [see Warnings and Precautions (5.1, 5.3), Drug Interactions (7)].

Abuse may occur by taking intact tablets in quantities greater than prescribed or without legitimate purpose, by crushing and chewing or snorting the crushed formulation, or by injecting a solution made from the crushed formulation. Taking cut, broken, chewed, crushed, or dissolved HYSINGLA ER increases the risk of overdose and death.

HYSINGLA ER is approved for oral use only.

With parenteral abuse, the inactive ingredients in HYSINGLA ER can result in local tissue necrosis, infection, pulmonary granulomas, increased risk of endocarditis and valvular heart injury, embolism, and death. Parenteral drug abuse is commonly associated with transmission of infectious diseases such as hepatitis and HIV.

Abuse Deterrence Studies

HYSINGLA ER is formulated with physicochemical properties intended to make the tablet more difficult to manipulate for misuse and abuse, and maintains some extended-release characteristics even if the tablet is physically compromised. To evaluate the ability of these physicochemical properties to reduce the potential for abuse of HYSINGLA ER, a series of in vitro laboratory studies, pharmacokinetic studies and clinical abuse potential studies was conducted. A summary is provided at the end of this section.

In Vitro Testing

In vitro physical and chemical tablet manipulation studies were performed to evaluate the success of different extraction methods in defeating the extended-release formulation. Results support that HYSINGLA ER resists crushing, breaking, and dissolution using a variety of tools and solvents and retains some extended-release properties despite manipulation. When subjected to an aqueous environment, HYSINGLA ER gradually forms a viscous hydrogel (i.e., a gelatinous mass) that resists passage through a hypodermic needle.

Clinical Abuse Potential Studies

Studies in Non-dependent Opioid Abusers:

Two randomized, double-blind, placebo and active-comparator studies in non-dependent opioid abusers were conducted to characterize the abuse potential of HYSINGLA ER following physical manipulation and administration via the intranasal and oral routes. For both studies, drug liking was measured on a bipolar drug liking scale of 0 to 100 where 50 represents a neutral response of neither liking nor disliking, 0 represents maximum disliking, and 100 represents maximum liking. Response to whether the subject would take the study drug again was measured on a unipolar scale of 0 to 100 where 0 represents the strongest negative response ("definitely would not take drug again") and 100 represents the strongest positive response ("definitely would take drug again").

Intranasal Abuse Potential Study:

In the intranasal abuse potential study, 31 subjects were dosed and 25 subjects completed the study. Treatments studied included intranasally administered tampered HYSINGLA ER 60 mg tablets, powdered hydrocodone bitartrate 60 mg, and placebo. Incomplete dosing due to granules falling from the subjects' nostrils occurred in 82% (n = 23) of subjects receiving tampered HYSINGLA ER compared to no subjects with powdered hydrocodone or placebo.

The intranasal administration of tampered HYSINGLA ER was associated with statistically significantly lower mean and median scores for drug liking and take drug again (P<0.001 for both), compared with powdered hydrocodone as summarized in Table 4.

Table 4. Summary of Maximum Scores (Emax) on Drug Liking and Take Drug Again VAS Following intranasal Administration of HYSINGLA ER and Hydrocodone Powder in Non-dependent Opioid Abusers
VAS Scale (100 point) |  | HYSINGLA ER Manipulated | Hydrocodone Powder
Intranasal (n=25) |  | HYSINGLA ER Manipulated | Hydrocodone Powder
Drug Liking [Bipolar scale (0=maximum negative response, 50=neutral response, 100=maximum positive response)]
Mean (SE) |  | 65.4 (3.7) | 90.4 (2.6)
Median (Range) |  | 56 (50–100) | 100 (51–100)
Take Drug Again [Unipolar scale (0=maximum negative response, 100=maximum positive response)]
Mean (SE) |  | 36.4 (8.2) | 85.2 (5.0)
Median (Range) |  | 14 (0-100) | 100 (1-100)

Figure 1 demonstrates a comparison of peak drug liking scores for tampered HYSINGLA ER compared with powdered hydrocodone in subjects (n = 25) who received both treatments intranasally. The Y-axis represents the percent of subjects attaining a percent reduction in peak drug liking scores for tampered HYSINGLA ER vs. hydrocodone powder greater than or equal to the value on the X-axis.

Approximately 80% (n = 20) of subjects had some reduction in drug liking with tampered HYSINGLA ER relative to hydrocodone powder. Sixty-eight percent (n = 17) of subjects had a reduction of at least 30% in drug liking with tampered HYSINGLA ER compared with hydrocodone powder, and approximately 64% (n = 16) of subjects had a reduction of at least 50% in drug liking with tampered HYSINGLA ER compared with hydrocodone powder. Approximately 20% (n = 5) of subjects had no reduction in liking with tampered HYSINGLA ER relative to hydrocodone powder.

Figure 1: Percent Reduction Profiles for Emax of Drug Liking VAS for Manipulated HYSINGLA ER vs. Hydrocodone Powder, N = 25 Following Intranasal Administration

Oral Abuse Potential Study:

In the oral abuse potential study, 40 subjects were dosed and 35 subjects completed the study. Treatments studied included oral administrations of chewed HYSINGLA ER 60 mg tablets, intact HYSINGLA ER 60 mg tablets, 60 mg aqueous hydrocodone bitartrate solution, and placebo.

The oral administration of chewed and intact HYSINGLA ER was associated with statistically lower mean and median scores on scales that measure drug liking and desire to take drug again (P<0.001), compared to hydrocodone solution as summarized in Table 5.

Table 5. Summary of Maximum Scores (Emax) on Drug Liking and Take Drug Again VAS Following Oral Administration of HYSINGLA ER and Hydrocodone Solution in Non-dependent Recreational Opioid Users
VAS Scale (100 point) |  | HYSINGLA ER |  | Hydrocodone Solution
Oral (n=35) |  | Intact | Chewed | Hydrocodone Solution
Drug Liking [Bipolar scale (0=maximum negative response, 50=neutral response, 100=maximum positive response)]
Mean (SE) |  | 63.3 (2.7) | 69.0 (3.0) | 94.0 (1.7)
Median (Range) |  | 58 (50–100) | 66 (50–100) | 100 (51–100)
Take Drug Again [Unipolar scale (0=maximum negative response, 100=maximum positive response)]
Mean (SE) |  | 34.3 (6.1) | 44.3 (6.9) | 89.7 (3.6)
Median (Range) |  | 24 (0-100) | 55 (0-100) | 100 (1-100)

Figure 2 demonstrates a comparison of peak drug liking scores for chewed HYSINGLA ER compared with hydrocodone solution in subjects who received both treatments orally. The Y-axis represents the percent of subjects attaining a percent reduction in peak drug liking scores for chewed HYSINGLA ER vs. hydrocodone solution greater than or equal to the value on the X-axis.

Approximately 80% (n = 28) of subjects had some reduction in drug liking with chewed HYSINGLA ER relative to hydrocodone solution. Approximately 69% (n = 24) of subjects had a reduction of at least 30% in drug liking with chewed HYSINGLA ER compared with hydrocodone solution, and approximately 60% (n = 21) of subjects had a reduction of at least 50% in drug liking with chewed HYSINGLA ER compared with hydrocodone solution. Approximately 20% (n = 7) of subjects had no reduction in drug liking with chewed HYSINGLA ER relative to hydrocodone solution.

Figure 2: Percent Reduction Profiles for Emax of Drug Liking VAS for Chewed HYSINGLA ER vs. Hydrocodone Solution, N = 35 Following Oral Administration

The results of a similar analysis of drug liking for intact HYSINGLA ER relative to hydrocodone solution were comparable to the results of chewed HYSINGLA ER relative to hydrocodone solution. Approximately 83% (n = 29) of subjects had some reduction in drug liking with intact HYSINGLA ER relative to hydrocodone solution. Eighty-three percent (n = 29) of subjects had a reduction of at least 30% in peak drug liking scores with intact HYSINGLA ER compared to hydrocodone solution, and approximately 74% (n = 26) of subjects had a reduction of at least 50% in peak drug liking scores with intact HYSINGLA ER compared with hydrocodone solution. Approximately 17% (n = 6) had no reduction in drug liking with intact HYSINGLA ER relative to hydrocodone solution.

Summary

The in vitro data demonstrate that HYSINGLA ER has physical and chemical properties that are expected to deter intranasal and intravenous abuse. The data from the clinical abuse potential studies, along with support from the in vitro data, also indicate that HYSINGLA ER has physicochemical properties that are expected to reduce intranasal abuse and oral abuse when chewed. However, abuse of HYSINGLA ER by the intravenous, intranasal, and oral routes is still possible.

Additional data, including epidemiological data, when available, may provide further information on the impact of HYSINGLA ER on the abuse liability of the drug. Accordingly, this section may be updated in the future as appropriate.

9.3 Dependence

Both tolerance and physical dependence can develop during use of opioid therapy.

Tolerance is a physiological state characterized by a reduced response to a drug after repeated administration (i.e., a higher dose of a drug is required to produce the same effect that was once obtained at a lower dose).

Physical dependence is a state that develops as a result of a physiological adaptation in response to repeated drug use, manifested by withdrawal signs and symptoms after abrupt discontinuation or a significant dose reduction of a drug.

Withdrawal may be precipitated through the administration of drugs with opioid antagonist activity (e.g., naloxone, nalmefene), mixed agonist/antagonist analgesics (e.g., pentazocine, butorphanol, nalbuphine), or partial agonists (e.g., buprenorphine). Physical dependence may not occur to a clinically significant degree until after several days to weeks of continued use.

Do not rapidly reduce or abruptly discontinue HYSINGLA ER in a patient physically dependent on opioids. Rapid tapering of HYSINGLA ER in a patient physically dependent on opioids may lead to serious withdrawal symptoms, uncontrolled pain, and suicide. Rapid discontinuation has also been associated with attempts to find other sources of opioid analgesics, which may be confused with drug-seeking for abuse.

When discontinuing HYSINGLA ER, gradually taper the dosage using a patient-specific plan that considers the following: the dose of HYSINGLA ER the patient has been taking, the duration of treatment, and the physical and psychological attributes of the patient. To improve the likelihood of a successful taper and minimize withdrawal symptoms, it is important that the opioid tapering schedule is agreed upon by the patient. In patients taking opioids for an extended period of time at high doses, ensure that a multimodal approach to pain management, including mental health support (if needed), is in place prior to initiating an opioid analgesic taper [see Dosage and Administration (2.7), Warnings and Precautions (5.16)].

Infants born to mothers physically dependent on opioids will also be physically dependent and may exhibit respiratory difficulties and withdrawal signs [see Use in Specific Populations (8.1)].

10 OVERDOSAGE

Clinical Presentation

Acute overdosage with hydrocodone can be manifested by respiratory depression, somnolence progressing to stupor or coma, skeletal muscle flaccidity, cold and clammy skin, constricted pupils, and, in some cases, pulmonary edema, bradycardia, hypotension, hypoglycemia, partial or complete airway obstruction, atypical snoring, and death. Marked mydriasis rather than miosis may be seen with hypoxia in overdose situations [see Clinical Pharmacology (12.2)]. Toxic leukoencephalopathy has been reported after opioid overdose and can present hours, days, or weeks after apparent recovery from the initial intoxication.

Treatment of Overdose

In case of overdose, priorities are the re-establishment of a patent airway and institution of assisted or controlled ventilation, if needed. Employ other supportive measures (including oxygen and vasopressors) in the management of circulatory shock and pulmonary edema accompanying overdose as indicated. Cardiac arrest or arrhythmias will require advanced life support measures.

For clinically significant respiratory or circulatory depression secondary to hydrocodone overdose, administer an opioid overdose reversal agent such as naloxone or nalmefene.

Because the duration of opioid reversal is expected to be less than the duration of action of hydrocodone in HYSINGLA ER, carefully monitor the patient until spontaneous respiration is reliably re-established. HYSINGLA ER will continue to release hydrocodone and add to the hydrocodone load for 24 to 48 hours or longer following ingestion, necessitating prolonged monitoring. If the response to an opioid overdose reversal agent is suboptimal or only brief in nature, administer additional reversal agent as directed by the product's prescribing information.

In an individual physically dependent on opioids, administration of the recommended dose of the opioid overdose reversal agent will precipitate an acute withdrawal syndrome. The severity of the withdrawal syndrome produced will depend on the degree of physical dependence and the dose of the reversal agent administered. If a decision is made to treat serious respiratory depression in the physically dependent patient, administration of the reversal agent should be initiated with care and by titration with smaller than usual doses of the reversal agent.

11 DESCRIPTION

HYSINGLA ER (hydrocodone bitartrate) extended-release tablets are supplied in 20 mg, 30 mg, 40 mg, 60 mg, 80 mg, 100 mg and 120 mg film-coated tablets for oral administration. The tablet strengths describe the amount of hydrocodone per tablet as the bitartrate salt.

Hydrocodone bitartrate is an opioid agonist. Its chemical name is 4,5α-epoxy-3-methoxy-17-methylmorphinan-6-one tartrate (1:1) hydrate (2:5). Its structural formula is:

Empirical formula: C18H21NO3 ∙ C4H6O6 ∙ 2½H2O;

Molecular weight: 494.49.

Hydrocodone bitartrate exists as fine white crystals or a crystalline powder. It is affected by light. It is soluble in water, slightly soluble in alcohol, and insoluble in ether and chloroform.

The 20 mg, 30 mg, 40 mg, 60 mg, 80 mg, 100 mg and 120 mg tablets contain the following inactive ingredients: Butylated Hydroxytoluene (BHT, an additive in Polyethylene Oxide), Hydroxypropyl Cellulose, Macrogol/PEG 3350, Magnesium Stearate, Microcrystalline Cellulose, Polyethylene Oxide, Polysorbate 80, Polyvinyl Alcohol, Talc, Titanium Dioxide, and Black Ink.

The 20 mg tablets also contain Iron Oxide Yellow and FD&C Blue #2 Aluminum Lake/Indigo Carmine Aluminum Lake.

The 30 mg tablets also contain Iron Oxide Yellow.

The 40 mg tablets also contain Iron Oxide Yellow, Iron Oxide Red, and Iron Oxide Black.

The 60 mg tablets also contain Iron Oxide Yellow and Iron Oxide Red.

The 80 mg tablets also contain Iron Oxide Red.

The 100 mg tablets also contain FD&C Blue #2 Aluminum Lake.

Black Ink Contains: Shellac Glaze (in Ethanol), Isopropyl Alcohol, Iron Oxide Black, N-Butyl Alcohol, Propylene Glycol and Ammonium Hydroxide.

12 CLINICAL PHARMACOLOGY

12.1 Mechanism of Action

Hydrocodone is a full opioid agonist with relative selectivity for the mu-opioid receptor, although it can interact with other opioid receptors at higher doses. The principal therapeutic action of hydrocodone is analgesia. Like all full opioid agonists, there is no ceiling effect for analgesia with hydrocodone. Clinically, dosage is titrated to provide adequate analgesia and may be limited by adverse reactions, including respiratory and CNS depression.

The precise mechanism of the analgesic action is unknown. However, specific CNS opioid receptors for endogenous compounds with opioid-like activity have been identified throughout the brain and spinal cord and are thought to play a role in the analgesic effects of this drug.

12.2 Pharmacodynamics

Cardiac Electrophysiology

QTc interval prolongation was studied in a double-blind, placebo- and positive-controlled 3-treatment parallel-group, dose-escalating study of HYSINGLA ER in 196 healthy subjects. QTc interval prolongation was observed following HYSINGLA ER 160 mg per day. The maximum mean (90% upper confidence bound) difference in the QTc interval between HYSINGLA ER and placebo (after baseline-correction) at steady state was 6 (9) milliseconds, 7 (10) milliseconds, and 10 (13) milliseconds at HYSINGLA ER doses of 80 mg, 120 mg and 160 mg respectively. For clinical implications of the prolonged QTc interval, [see Warnings and Precautions (5.11)].

Effects on the Central Nervous System

Hydrocodone produces respiratory depression by direct action on brainstem respiratory centers. The respiratory depression involves a reduction in the responsiveness of the brain stem respiratory centers to both increases in carbon dioxide tension and electrical stimulation.

Hydrocodone causes miosis, even in total darkness. Pinpoint pupils are a sign of opioid overdose but are not pathognomonic (e.g., pontine lesions of hemorrhagic or ischemic origin may produce similar findings). Marked mydriasis rather than miosis may be seen with hypoxia in overdose situations [see Overdosage (10)].

Effects on the Gastrointestinal Tract and Other Smooth Muscle

Hydrocodone causes a reduction in motility associated with an increase in smooth muscle tone in the antrum of the stomach and duodenum. Digestion of food in the small intestine is delayed and propulsive contractions are decreased. Propulsive peristaltic waves in the colon are decreased, while tone is increased to the point of spasm, resulting in constipation. Other opioid-induced effects may include a reduction in biliary and pancreatic secretions, spasm of sphincter of Oddi, transient elevations in serum amylase, and opioid-induced esophageal dysfunction (OIED).

Effects on the Cardiovascular System

Hydrocodone produces peripheral vasodilation, which may result in orthostatic hypotension or syncope Manifestations of histamine release and/or peripheral vasodilation may include pruritus, flushing, red eyes, sweating, and/or orthostatic hypotension.

Effects on the Endocrine System

Opioids inhibit the secretion of adrenocorticotropic hormone (ACTH), cortisol, and luteinizing hormone (LH) in humans [see Adverse Reactions (6.2)]. They also stimulate prolactin, growth hormone (GH) secretion, and pancreatic secretion of insulin and glucagon.

Use of opioids for an extended period of time may influence the hypothalamic-pituitary-gonadal axis, leading to androgen deficiency that may manifest as low libido, impotence, erectile dysfunction, amenorrhea, or infertility. The causal role of opioids in the clinical syndrome of hypogonadism is unknown because the various medical, physical, lifestyle, and psychological stressors that may influence gonadal hormone levels have not been adequately controlled for in studies conducted to date [see Adverse Reactions (6.2)].

Effects on the Immune System

Opioids have been shown to have a variety of effects on components of the immune system in in vitro and animal models. The clinical significance of these findings is unknown. Overall, the effects of opioids appear to be modestly immunosuppressive.

Concentration—Efficacy Relationships

The minimum effective analgesic concentration will vary widely among patients especially among patients who have been previously treated with opioid agonists. The minimum effective analgesic concentration of hydrocodone for any individual patient may increase over time due to an increase in pain, the development of a new pain syndrome, and/or the development of analgesic tolerance [see Dosage and Administration (2.1, 2.4)].

Concentration—Adverse Experience Relationships

There is a relationship between increasing hydrocodone plasma concentration and increasing frequency of adverse reactions such as nausea, vomiting, CNS effects, and respiratory depression. In opioid-tolerant patients, the situation may be altered by the development of tolerance to opioid-related adverse reactions [see Dosage and Administration (2.1, 2.3, 2.4)].

12.3 Pharmacokinetics

Absorption

HYSINGLA ER is a single-entity extended-release formulation of hydrocodone that yields a gradual increase in plasma hydrocodone concentrations with a median Tmax of 14 – 16 hours noted for different dose strengths. Peak plasma levels may occur in the range of 6 -30 hours after single-dose HYSINGLA ER administration.

Systemic exposure (AUC and Cmax) increased linearly with doses from 20 to 120 mg. Both Cmax and AUC increased slightly more than dose proportionally (Table 6). The mean terminal half-life (t1/2) was similar for all HYSINGLA ER dose strengths ranging from 7 to 9 hours.

Table 6 Mean (SD) Single-Dose Pharmacokinetic Parameters of HYSINGLA ER
Dose Strength (mg) | AUCinf (ng∙h/mL) | Cmax (ng/mL) | Tmax [median (minimum, maximum)] (h)
20 | 284 (128) | 14.6 (5.5) | 16 (6, 24)
40 | 622 (252) | 33.9 (11.8) | 16 (6, 24)
60 | 1009 (294) | 53.6 (15.4) | 14 (10, 30)
80 | 1304 (375) | 69.1 (17.2) | 16 (10, 24)
120 | 1787 (679) | 110 (44.1) | 14 (6, 30)

As compared to an immediate-release hydrocodone combination product, HYSINGLA ER at the same daily dose results in similar bioavailability but with lower maximum concentrations at steady state (Figure 3).

Figure 3: Mean Steady-State Plasma Hydrocodone Concentration Profile

Steady-state plasma hydrocodone concentrations were confirmed on day 3 of once-daily dosing of HYSINGLA ER. The extent of accumulation of systemic exposure was 1.3 and 1.1 fold with respect to AUC and Cmax at steady-state. The mean terminal half-life (t1/2) at steady state was 7 hours. Median Tmax values were 14 hours (range: 12 to 24 hours) on both Day 1 and Day 5 following once daily administration of HYSINGLA ER for five days. Daily fluctuation in peak to trough plasma levels of hydrocodone were higher at 80 mg and 120 mg doses of HYSINGLA ER compared to 30 mg dose (Table 7).

Table 7. Mean (SD) Steady-State Hydrocodone Pharmacokinetic Parameters
Regimen | AUC24,ss (ng∙h/mL) | Cmax,ss (ng/mL) | Cmin,ss (ng/mL) | %Fluctuation [Mean (minimum, maximum); Percentage fluctuation in plasma concentration is derived as (Cmax,ss – Cmin, ss)*100/Cavg,ss.]
HYSINGLA ER
30 mg q24h | 443 (128) | 26.4 (7.4) | 16.7 (5.2) | 61 (6.4,113)
80 mg q24h | 1252 (352) | 82.6 (25.7) | 28.2 (12) | 105 (36,214)
120 mg q24h | 1938 (729) | 135 (50) | 63.6 (29) | 97.9 (32, 250)

Food Effects

Cmax and AUC of HYSINGLA ER 120 mg tablets were similar under low fat conditions relative to fasting conditions (17% and 9% higher, respectively). Cmax was higher (54%) under high fat conditions relative to fasting conditions; however, AUC of HYSINGLA ER 120 mg tablets was only 20% higher when co-administered with a high fat meal. HYSINGLA ER may be administered without regard to meals.

Distribution

Following administration of HYSINGLA ER, the typical (70 kg adult) value of apparent volume of distribution (V/F) is 402 L, suggesting extensive tissue distribution. The extent of in vivo binding of hydrocodone to human plasma proteins was minimal with a mean % bound at 36%.

Elimination

Metabolism

Hydrocodone exhibits a complex pattern of metabolism, including N-demethylation, O-demethylation, and 6-keto reduction to the corresponding 6-α-and 6-β-hydroxy metabolites. CYP3A4 mediated N-demethylation to inactive norhydrocodone is the primary metabolic pathway of hydrocodone with a lower contribution from CYP2B6 and CYP2C19. The minor metabolite hydromorphone (<3% of the circulating parent hydrocodone) was mainly formed by CYP2D6 mediated O-demethylation with a smaller contribution by CYP2B6 and CYP2C19. Hydromorphone may contribute to the total analgesic effect of hydrocodone.

Excretion

Hydrocodone and its metabolites are cleared primarily by renal excretion. The percent of administered dose excreted unchanged as hydrocodone in urine was 6.5% in subjects with normal renal function, and 5.0%, 4.8%, and 2.3% in subjects with mild, moderate, and severe renal impairment, respectively. Renal clearance (CLr) of hydrocodone in healthy subjects was small (5.3 L/h) compared to apparent oral clearance (CL/F, 83 L/h); suggesting that non-renal clearance is the main elimination route. Ninety-nine percent of the administered dose is eliminated within 72 hours. The mean terminal half-life (t1/2) was similar for all HYSINGLA ER dose strengths ranging from approximately 7 to 9 hours across the range of doses.

Specific Populations

Age: Geriatric Patients

Following administration of 40 mg HYSINGLA ER, the pharmacokinetics of hydrocodone in healthy elderly subjects (65 to 77 years) are similar to the pharmacokinetics in healthy younger subjects (20 to 45 years). There were no clinically meaningful increase in Cmax (16%) and AUC (15%) of hydrocodone in elderly as compared with younger adult subjects [see Use in Specific Populations (8.5)].

Sex

Systemic exposure of hydrocodone (Cmax and AUC) was similar between males and females.

Hepatic Impairment

After a single dose of 20 mg HYSINGLA ER in subjects (8 each) with normal hepatic function, mild, moderate or severe hepatic impairment based on Child-Pugh classifications, mean hydrocodone Cmax values were 16, 15, 17, and 18 ng/mL, respectively. Mean hydrocodone AUC values were 342, 310, 390, and 415 ng.hr/mL for subjects with normal hepatic function, mild, moderate or severe hepatic impairment, respectively. Geometric mean hydrocodone Cmax values were -6%, 5%, and 5% and AUC values were -14%, 13%, and 4% in patients with mild, moderate or severe hepatic impairment, respectively, when compared with subjects with normal hepatic function.

The mean in vivo plasma protein binding of hydrocodone across the groups was similar, ranging from 33% to 37% [see Use in Specific Populations (8.6)].

Renal Impairment

After a single dose of 60 mg HYSINGLA ER in subjects (8 each) with normal renal function, mild, moderate, or severe renal impairment based on Cockcroft-Gault criteria and end stage renal disease (with dialysis) patients, mean hydrocodone Cmax values were 40, 50, 51, 46, and 38 ng/mL, respectively. Mean hydrocodone AUC values were 754, 942, 1222, 1220, and 932 ng.hr/mL for subjects with normal renal function, mild, moderate or severe renal impairment and ESRD with dialysis, respectively. Hydrocodone Cmax values were 14%, 23%, 11% and -13% and AUC values were 13%, 61%, 57% and 4% higher in patients with mild, moderate or severe renal impairment or end stage renal disease with dialysis, respectively [see Use in Specific Populations (8.7)].

Drug Interaction Studies

CYP3A4

Co-administration of HYSINGLA ER (20 mg single dose) and CYP3A4 inhibitor ketoconazole (200 mg BID for 6 days) increased mean hydrocodone AUC and Cmax by 135% and 78%, respectively [see Warnings and Precautions (5.6) and Drug Interactions (7)].

CYP2D6

The 90% confidence interval (CI) of the geometric means for hydrocodone AUCinf (98 to 115%), AUCt (98 to 115%), and Cmax (93 to 121%) values were within the range of 80 to 125% when a single dose of HYSINGLA ER 20 mg was co-administered with CYP2D6 inhibitor paroxetine (20 mg treatment each morning for 12 days). No differences in systemic exposure of hydrocodone were observed in the presence of paroxetine.

13 NONCLINICAL TOXICOLOGY

13.1 Carcinogenesis, Mutagenesis, Impairment of Fertility

Carcinogenesis

Hydrocodone was evaluated for carcinogenic potential in rats and mice. In a two-year bioassay in rats, doses up to 25 mg/kg in males and females were administered orally and no treatment-related neoplasms were observed (exposure is equivalent to 0.2 times the human hydrocodone dose of 120 mg/day based on AUC exposure comparisons). In a two-year bioassay in mice, doses up to 200 mg/kg in males and 100 mg/kg in females were administered orally and no treatment-related neoplasms were observed (exposure is equivalent to 3.5 times and 3.0 times, respectively, the human hydrocodone dose of 120 mg/day based on AUC exposure comparisons).

Mutagenesis

Hydrocodone was genotoxic in the mouse lymphoma assay in the presence of rat S9 metabolic activation but not in the absence of rat metabolic activation. However, hydrocodone was not genotoxic in the mouse lymphoma assay with or without human S9 metabolic activation. There was no evidence of genotoxic potential with hydrocodone in an in vitro bacterial reverse mutation assay with Salmonella typhimurium and Escherichia coli with or without metabolic activation or in an in vivo mouse bone marrow micronucleus test with or without metabolic activation.

Impairment of Fertility

No effect on fertility or general reproductive performance was seen with oral administration of hydrocodone to male and female rats at doses up to 25 mg/kg/day (approximately 0.06 times and 0.08 times, respectively, the human hydrocodone dose of 120 mg/day based on AUC exposure comparisons).

14 CLINICAL STUDIES

14.1 Moderate to Severe Chronic Lower Back Pain Study

The efficacy and safety of HYSINGLA ER was evaluated in a randomized double-blind, placebo-controlled, multi-center, 12-week clinical trial in both opioid-experienced patients and patients who were not opioid tolerant with moderate to severe chronic low back pain.

A total of 905 chronic low back pain patients (opioid naive and opioid-experienced) who were not responsive to their prior analgesic therapy entered an open-label conversion and dose- titration period for up to 45 days with HYSINGLA ER. Patients were dosed once daily with HYSINGLA ER (20 to 120 mg). Patients stopped their prior opioid analgesics and/or nonopioid analgesics prior to starting HYSINGLA ER treatment. Optional use of rescue medication (immediate-release oxycodone 5 mg) up to 2 doses (2 tablets) was permitted during the dose titration period. For inadequately controlled pain, HYSINGLA ER dose was allowed to be increased once every 3–5 days until a stabilized and tolerable dose was identified. During the dose-titration period, 65% of the patients achieved a stable HYSINGLA ER dose and entered the double-blind treatment period. The remaining subjects discontinued from the dose-titration period for the following reasons: adverse events (10%); lack of therapeutic effect (5%); confirmed or suspected diversion (3%); subject's choice (5%); lost to follow-up (2%); administrative reasons (2%); and failure to achieve protocol-defined reduction in pain score (7%).

Following the dose titration period, 588 patients (65%) were randomized at a ratio of 1:1 into a 12-week double-blind treatment period with their fixed stabilized dose of HYSINGLA ER (or matching placebo). These patients met the study randomization criteria of adequate analgesia (pain reduction of at least 2 points to a score of 4 or less on a 0-10 numerical rating scale) and acceptable tolerability of HYSINGLA ER. Patients randomized to placebo were given a blinded taper of HYSINGLA ER according to a pre-specified tapering schedule, 3 days on each step-down dose (reduced by 25-50% from the previous dose). Patients were allowed to use rescue medication (immediate-release oxycodone 5 mg) up to 6 doses (6 tablets) per day depending on their randomized HYSINGLA ER dose. During the double-blind period, 229 treated patients (77%) completed the 12-week treatment with HYSINGLA ER and 210 patients (72%) completed on placebo. Overall, 10% of patients discontinued due to lack of therapeutic effect (5% in HYSINGLA patients and 15% in placebo patients); 5% of patients discontinued due to adverse events (6% in HYSINGLA ER treated patients and 3% in placebo patients).

HYSINGLA ER provided greater analgesia compared with placebo. There was a statistically significant difference in the weekly average pain scores at Week 12 between the two groups.

The percentage of patients (responders) in each group who demonstrated improvement in their weekly average pain scores at Week 12, as compared with screening is shown in Figure 4. The figure is cumulative, so that patients whose change from screening is, for example, 30%, are also included at every level of improvement below 30%. Patients who did not complete the study were classified as non-responders. Treatment with HYSINGLA ER resulted in a higher proportion of responders, defined as patients with at least a 30% and 50% improvement, as compared with placebo.

Figure 4. Percent Improvement in Pain Intensity

16 HOW SUPPLIED/STORAGE AND HANDLING

HYSINGLA ER (hydrocodone bitartrate) extended-release tablets 20 mg are round, green-colored, bi-convex tablets printed with "HYD 20" and are supplied in child-resistant closure, opaque plastic bottles of 60 (NDC 59011-271-60).

HYSINGLA ER (hydrocodone bitartrate) extended-release tablets 30 mg are round, yellow-colored, bi-convex tablets printed with "HYD 30" and are supplied in child-resistant closure, opaque plastic bottles of 60 (NDC 59011-272-60).

HYSINGLA ER (hydrocodone bitartrate) extended-release tablets 40 mg are round, grey-colored, bi-convex tablets printed with "HYD 40" and are supplied in child-resistant closure, opaque plastic bottles of 60 (NDC 59011-273-60).

HYSINGLA ER (hydrocodone bitartrate) extended-release tablets 60 mg are round, beige-colored, bi-convex tablets printed with "HYD 60" and are supplied in child-resistant closure, opaque plastic bottles of 60 (NDC 59011-274-60).

HYSINGLA ER (hydrocodone bitartrate) extended-release tablets 80 mg are round, pink-colored, bi-convex tablets printed with "HYD 80" and are supplied in child-resistant closure, opaque plastic bottles of 60 (NDC 59011-275-60).

HYSINGLA ER (hydrocodone bitartrate) extended-release tablets 100 mg are round, blue-colored, bi-convex tablets printed with "HYD 100" and are supplied in child-resistant closure, opaque plastic bottles of 60 (NDC 59011-276-60).

HYSINGLA ER (hydrocodone bitartrate) extended-release tablets 120 mg are round, white-colored, bi-convex tablets printed with "HYD 120" and are supplied in child-resistant closure, opaque plastic bottles of 60 (NDC 59011-277-60).

STORAGE AND HANDLING

Store at 25°C (77°F); excursions permitted between 15°-30°C (59°-86°F) [see USP Controlled Room Temperature].

Dispense in tight, light-resistant container, as defined by the USP.

Store HYSINGLA ER securely and dispose of properly.

17 PATIENT COUNSELING INFORMATION

Advise the patient to read the FDA-approved patient labeling (Medication Guide)

Storage and Disposal:

Because of the risks associated with accidental ingestion, misuse, and abuse, advise patients to store HYSINGLA ER securely, out of sight and reach of children, and in a location not accessible by others, including visitors to the home. Inform patients that leaving HYSINGLA ER unsecured can pose a deadly risk to others in the home [see Warnings and Precautions (5.1, 5.2), Drug Abuse and Dependence (9.2)].

Advise patients and caregivers that when medicines are no longer needed, they should be disposed of promptly. Expired, unwanted, or unused HYSINGLA ER should be disposed of by flushing the unused medication down the toilet if a drug take-back option is not readily available. Inform patients that they can visit www.fda.gov/drugdisposal for a complete list of medicines recommended for disposal by flushing, as well as additional information on disposal of unused medicines.

Addiction, Abuse, and Misuse

Inform patients that the use of HYSINGLA ER, even when taken as recommended, can result in addiction, abuse, and misuse, which can lead to overdose or death [see Warnings and Precautions (5.1)]. Instruct patients not to share HYSINGLA ER with others and to take steps to protect HYSINGLA ER from theft or misuse.

Life-Threatening Respiratory Depression

Inform patients of the risk of life-threatening respiratory depression, including information that the risk is greatest when starting HYSINGLA ER or when the dosage is increased, and that it can occur even at recommended dosages.

Educate patients and caregivers on how to recognize respiratory depression and emphasize the importance of calling 911 or getting emergency medical help right away in the event of a known or suspected overdose [see Warnings and Precautions (5.2), Overdosage (10)].

Accidental Ingestion

Inform patients that accidental ingestion, especially by children, may result in respiratory depression or death [see Warnings and Precautions (5.2)].

Interaction with Benzodiazepines and other CNS Depressants

Inform patients and caregivers that potentially fatal additive effects may occur if HYSINGLA ER is used with benzodiazepines or other CNS depressants, including alcohol (e.g., non-benzodiazepine sedative/hypnotics, anxiolytics, tranquilizers, muscle relaxants, general anesthetics, antipsychotics, gabapentinoids [gabapentin or pregabalin], and other opioids), and not to use these concomitantly unless supervised by a health care provider [see Warnings and Precautions (5.3), Drug Interactions (7)].

Patient Access to an Opioid Overdose Reversal Agent for the Emergency Treatment of Opioid Overdose

Inform patients and caregivers about opioid overdose reversal agents (e.g., naloxone, nalmefene). Discuss the importance of having access to an opioid overdose reversal agent, especially if the patient has risk factors for overdose (e.g., concomitant use of CNS depressants, a history of opioid use disorder, or prior opioid overdose) or if there are household members (including children) or other close contacts at risk for accidental ingestion or opioid overdose.

Discuss with the patient the options for obtaining an opioid overdose reversal agent (e.g., prescription, over-the-counter, or as part of a community-based program) [see Dosage and Administration (2.2), Warnings and Precautions (5.3)].

Educate patients and caregivers on how to recognize the signs and symptoms of an overdose.

Explain to patients and caregivers that effects of opioid overdose reversal agents like naloxone and nalmefene are temporary, and that they must call 911 or get emergency medical help right away in all cases of known or suspected opioid overdose, even if an opioid overdose reversal agent is administered [see Overdosage (10)].

Advise patients and caregivers:

- how to treat with the opioid overdose reversal agent in the event of an opioid overdose.
- to tell family and friends about the overdose reversal agent and to keep it in a place where family and friends can access it in an emergency.
- to read the Patient Information (or other educational material) that will come with their opioid overdose reversal agent. Emphasize the importance of doing this before an opioid emergency happens, so the patient and caregiver will know what to do.

Hyperalgesia and Allodynia

Inform patients and caregivers not to increase opioid dosage without first consulting a clinician. Advise patients to seek medical attention if they experience symptoms of hyperalgesia, including worsening pain, increased sensitivity to pain, or new pain [see Warnings and Precautions (5.7), Adverse Reactions (6.2)].

Serotonin Syndrome

Inform patients that opioids could cause a rare but potentially life-threatening condition called serotonin syndrome resulting from concomitant administration of serotonergic drugs. Warn patients of the symptoms of serotonin syndrome and to seek medical attention right away if symptoms develop. Instruct patients to inform their healthcare providers if they are taking, or plan to take serotonergic medications [see Drug Interactions (7)].

MAOI Interaction

Inform patients to avoid taking HYSINGLA ER while using any drugs that inhibit monoamine oxidase. Patients should not start MAOIs while taking HYSINGLA ER [see Drug Interactions (7)].

Important Administration Instructions

Instruct patients how to properly take HYSINGLA ER, including the following:

- Use HYSINGLA ER exactly as prescribed to reduce the risk of life-threatening adverse reactions (e.g., respiratory depression) [see Warnings and Precautions (5.2)].
- Swallow tablets whole, one tablet at a time, with enough water to ensure swallowing immediately after placing in the mouth [see Dosage and Administration (2.1)].
- Do not pre-soak, lick, or otherwise wet the tablet prior to placing in the mouth [see Dosage and Administration (2.1)].
- Do not chew, crush, or dissolve the tablets [see Dosage and Administration (2.1)].

Important Discontinuation Instructions

In order to avoid developing withdrawal symptoms, instruct patients not to discontinue HYSINGLA ER without first discussing a tapering plan with the prescriber [see Dosage and Administration (2.7)].

Driving or Operating Heavy Machinery

Inform patients that HYSINGLA ER may impair the ability to perform potentially hazardous activities such as driving a car or operating heavy machinery. Blood levels of hydrocodone, in some patients, may be high at the end of 24 hours after repeated dose administration. Advise patients not to perform such tasks until they know how they will react to the medication [see Warnings and Precautions (5.17)].

Constipation

Advise patients of the potential for severe constipation, including management instructions and when to seek medical attention. Instruct patients to monitor their analgesic response following the use of strong laxatives and to contact the prescriber if changes are noted [see Adverse Reactions (6), Clinical Pharmacology (12.2)].

Adrenal Insufficiency

Inform patients that HYSINGLA ER could cause adrenal insufficiency, a potentially life-threatening condition. Adrenal insufficiency may present with non-specific symptoms and signs such as nausea, vomiting, anorexia, fatigue, weakness, dizziness, and low blood pressure. Advise patients to seek medical attention if they experience a constellation of these symptoms [see Warnings and Precautions (5.9)].

Hypotension

Inform patients that HYSINGLA ER may cause orthostatic hypotension and syncope. Instruct patients how to recognize symptoms of low blood pressure and how to reduce the risk of serious consequences should hypotension occur (e.g., sit or lie down, carefully rise from a sitting or lying position) [see Warnings and Precautions (5.10)].

QTc interval prolongation

Inform patients that QT prolongation has been observed with HYSINGLA ER [see Clinical Pharmacology (12.2)]. HYSINGLA ER should be avoided in patients with congenital long QT syndrome. Instruct patients with a history of congestive heart failure or bradyarrhythmias, and patients at risk for electrolyte abnormalities or who are taking other medications known to prolong the QT interval, that periodic monitoring of electrocardiograms and electrolytes may be necessary during therapy with HYSINGLA ER [see Warnings and Precautions (5.11)].

Anaphylaxis

Inform patients that anaphylaxis has been reported with ingredients contained in HYSINGLA ER. Advise patients how to recognize such a reaction and when to seek medical attention [see Contraindications (4), Adverse Reactions (6)].

Pregnancy

Neonatal Opioid Withdrawal Syndrome

Inform female patients of reproductive potential that use of HYSINGLA ER for an extended period of time during pregnancy can result in neonatal opioid withdrawal syndrome, which may be life-threatening if not recognized and treated [see Warnings and Precautions (5.4), Use in Specific Populations (8.1)].

Embryo-Fetal Toxicity

Inform female patients of reproductive potential that HYSINGLA ER can cause fetal harm and to inform their healthcare provider of a known or suspected pregnancy [see Use in Specific Populations (8.1)].

Lactation

Advise patients that breastfeeding is not recommended during treatment with HYSINGLA ER [see Use in Specific Populations (8.2)].

Infertility

Inform patients that chronic use of opioids for an extended period of time may cause reduced fertility. It is not known whether these effects on fertility are reversible [see Adverse Reactions (6.2) Use in Specific Populations (8.3)].

Healthcare professionals can telephone Purdue Pharma's Medical Services Department (1-888-726-7535) for information on this product.

Purdue Pharma L.P.
Stamford, CT 06901-3431

©2025 Purdue Pharma L.P.

U.S. Patent Numbers: 8,808,740; 9,084,816; 9,101,661; 9,095,614; 9,095,615; 9,393,206; 9,486,412; 9,486,413; 9,492,389; 9,492,390; 9,492,391; 9,545,380; 9,572,779; 9,744,136; 9,750,703; 9,763,886; 9,763,933; 9,770,416; 9,770,417; 9,775,809; 9,775,810; 9,861,584; 9,872,837 and 11,844,865

Medication Guide
HYSINGLA® ER (hye-SING-luh)
(hydrocodone bitartrate) extended-release tablets, CII

HYSINGLA ER is:

- A strong prescription pain medicine that contains an opioid (narcotic) that is used to manage severe and persistent pain that requires an extended treatment period with a daily opioid pain medicine, when other non-opioid pain medicines do not treat your pain well enough or you cannot tolerate them.
- A long-acting (extended-release) opioid pain medicine that can put you at risk for overdose and death. Even if you take your dose correctly as prescribed you are at risk for opioid addiction, abuse, and misuse that can lead to death.
- Not to be taken on an "as needed" basis.

Important information about HYSINGLA ER:

- Get emergency help or call 911 right away if you take too much HYSINGLA ER (overdose). When you first start taking HYSINGLA ER, when your dose is changed, or if you take too much (overdose), serious or life-threatening breathing problems that can lead to death may occur. Ask your healthcare provider about medicines like naloxone or nalmefene that can be used in an emergency to reverse and opioid overdose.
- Taking HYSINGLA ER with other opioid medicines, benzodiazepines, gabapentinoids (gabapentin or pregabalin), alcohol, or other central nervous system depressants (including street drugs) can cause severe drowsiness, decreased awareness, breathing problems, coma, and death.
- Never give anyone else your HYSINGLA ER. They could die from taking it. Selling or giving away HYSINGLA ER is against the law.
- Store HYSINGLA ER securely, out of sight and reach of children, and in a location not accessible by others, including visitors to the home.

Do not take HYSINGLA ER if you have:

- severe asthma, trouble breathing, or other lung problems.
- a bowel blockage or have narrowing of the stomach or intestines.

Before taking HYSINGLA ER, tell your healthcare provider if you have a history of:

- head injury, seizures
- liver, kidney, thyroid problems
- problems urinating

- pancreas or gallbladder problems
- heart rhythm problems (long QT syndrome)

- abuse of street or prescription drugs, alcohol addiction, opioid overdose, or mental health problems

Tell your healthcare provider if you are:

- noticing your pain getting worse. If your pain gets worse after you take HYSINGLA ER, do not take more of HYSINGLA ER without first talking to your healthcare provider. Talk to your healthcare provider if the pain that you have increases, if you feel more sensitive to pain, or if you have new pain after taking HYSINGLA ER.
- pregnant or planning to become pregnant. Use of HYSINGLA ER for an extended period of time during pregnancy can cause withdrawal symptoms in your newborn baby that could be life-threatening if not recognized and treated.
- breastfeeding. Not recommended during treatment with HYSINGLA ER. It may harm your baby.
- living in a household where there are small children or someone who has abused street or prescription drugs.
- taking prescription or over-the-counter medicines, vitamins, or herbal supplements. Taking HYSINGLA ER with certain other medicines can cause serious side effects and could lead to death.

When taking HYSINGLA ER:

- Do not change your dose. Take HYSINGLA ER exactly as prescribed by your healthcare provider. Use the lowest dose possible for the shortest time needed.
- Take your prescribed dose every 24 hours, at the same time every day. Do not take more than your prescribed dose in 24 hours. If you miss a dose, take your next dose at your usual time the next day.
- Swallow HYSINGLA ER whole. Do not cut, break, chew, crush, dissolve, snort, or inject HYSINGLA ER because this may cause you to overdose and die.
- HYSINGLA ER should be taken 1 tablet at a time. Do not pre-soak, lick, or wet the tablet before placing it in your mouth to avoid choking on the tablet.

Call your healthcare provider if the dose you are taking does not control your pain.

- Do not stop taking HYSINGLA ER without talking to your healthcare provider.
- Dispose of expired, unwanted, or unused HYSINGLA ER, by promptly flushing down the toilet, if a drug take-back option is not readily available. Visit www.fda.gov/drugdisposal for additional information on disposal of unused medicines.

While taking HYSINGLA ER, DO NOT:

- Drive or operate heavy machinery until you know how HYSINGLA ER affects you. HYSINGLA ER can make you sleepy, dizzy, or lightheaded.
- Drink alcohol or use prescription or over-the-counter medicines that contain alcohol. Using products containing alcohol during treatment with HYSINGLA ER may cause you to overdose and die.

The possible side effects of HYSINGLA ER are:

- constipation, nausea, sleepiness, vomiting, tiredness, headache, dizziness, abdominal pain. Call your healthcare provider if you have any of these symptoms and they are severe.

Get emergency medical help or call 911 right away if you have:

- trouble breathing, shortness of breath, fast heartbeat, chest pain, swelling of your face, tongue or throat, extreme drowsiness, light-headedness when changing positions, feeling faint, agitation, high body temperature, trouble walking, stiff muscles, or mental changes such as confusion.

These are not all the possible side effects of HYSINGLA ER. Call your healthcare provider for medical advice about side effects. You may report side effects to FDA at 1-800-FDA-1088. For more information go to dailymed.nlm.nih.gov.
Manufactured by: Purdue Pharma L.P., Stamford, CT 06901-3431, www.purduepharma.com or call 1-888-726-7535

This Medication Guide has been approved by the U.S. Food and Drug Administration.
Revised: 12/2025

PACKAGE LABEL

HYSINGLA ER 20 mg

PACKAGE LABEL

HYSINGLA ER 30 mg

PACKAGE LABEL

HYSINGLA ER 40 mg

PACKAGE LABEL

HYSINGLA ER 60 mg

PACKAGE LABEL

HYSINGLA ER 80 mg

PACKAGE LABEL

HYSINGLA ER 100 mg

PACKAGE LABEL

HYSINGLA ER 120 mg